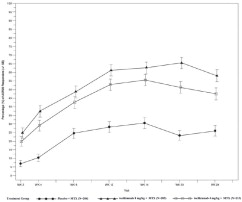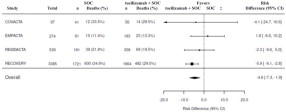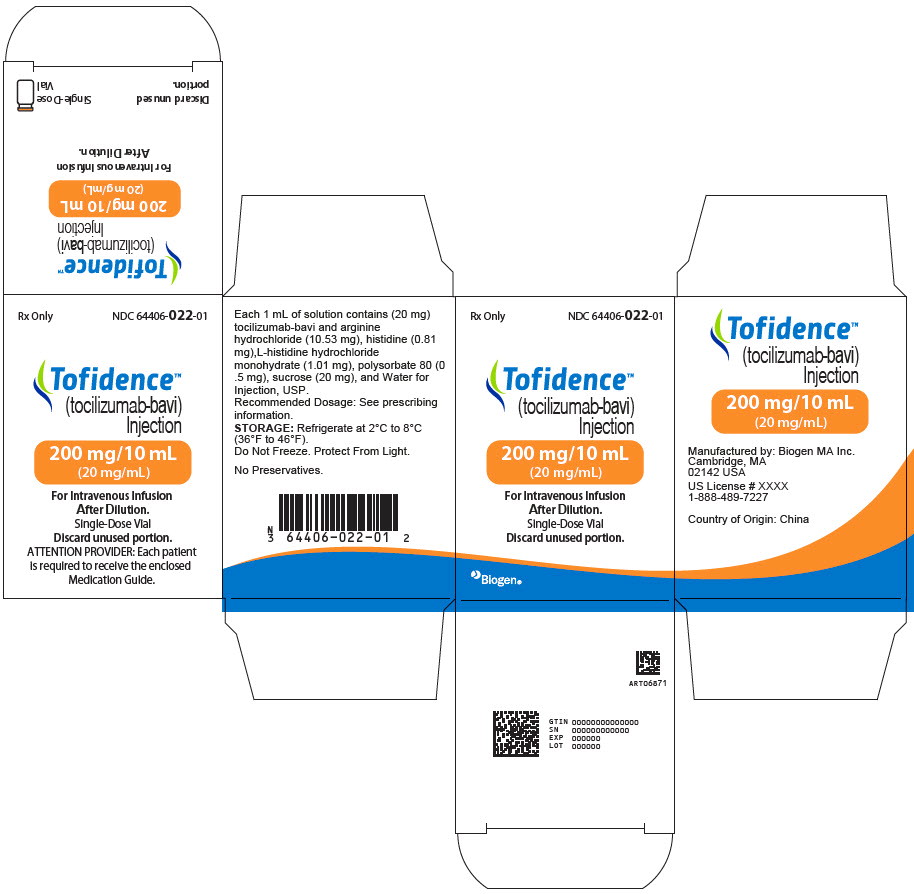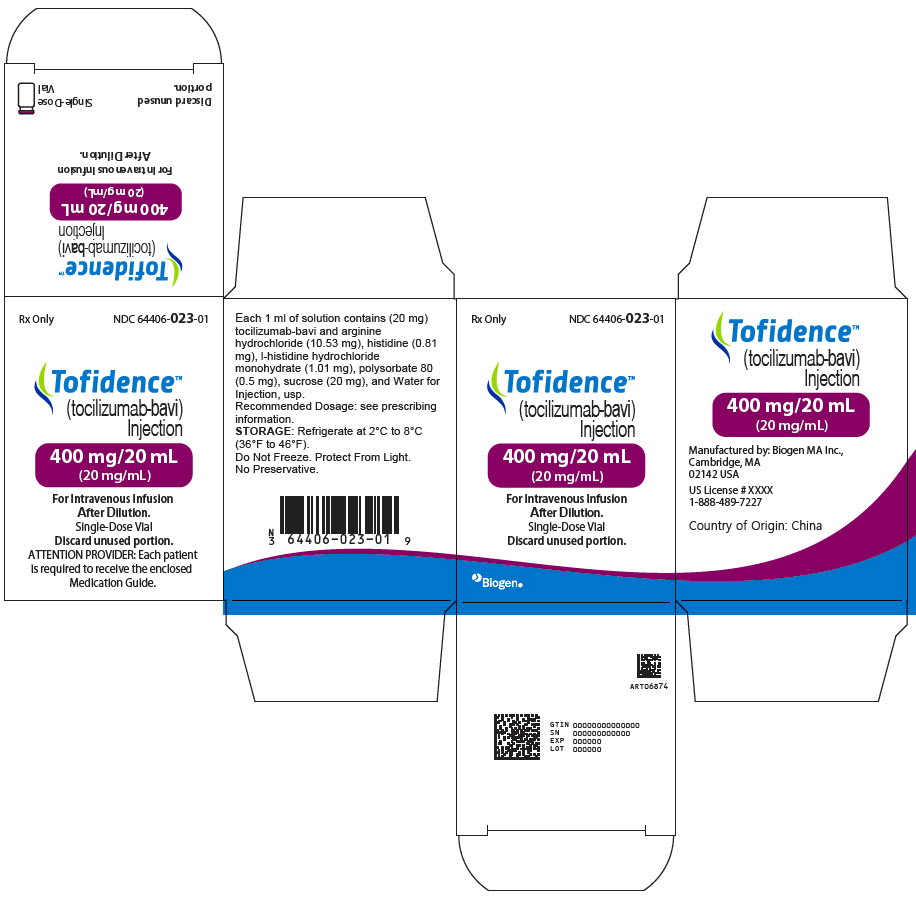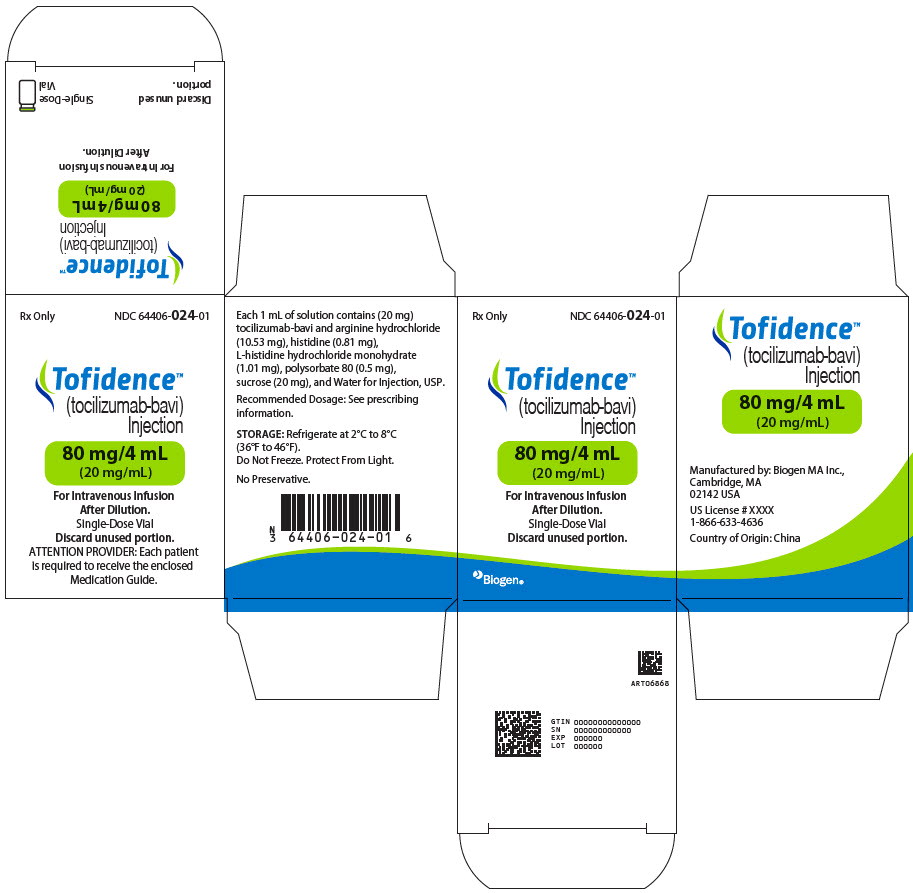 DRUG LABEL: Tofidence
NDC: 64406-022 | Form: INJECTION
Manufacturer: Biogen MA Inc
Category: prescription | Type: HUMAN PRESCRIPTION DRUG LABEL
Date: 20251219

ACTIVE INGREDIENTS: Tocilizumab 20 mg/1 mL
INACTIVE INGREDIENTS: HISTIDINE; HISTIDINE MONOHYDROCHLORIDE MONOHYDRATE; ARGININE HYDROCHLORIDE; SUCROSE; POLYSORBATE 80; WATER

HIGHLIGHTS OF PRESCRIBING INFORMATION

These highlights do not include all the information needed to use TOFIDENCE safely and effectively. See full prescribing information for TOFIDENCE.
TOFIDENCE™ (tocilizumab-bavi) injection, for intravenous use
Initial U.S. Approval: 2023
TOFIDENCE (tocilizumab-bavi) is biosimilar 1 to ACTEMRA (tocilizumab).
1 - Biosimilar means that the biological product is approved based on data demonstrating that it is highly similar to an FDA-approved biological product, known as a reference product, and that there are no clinically meaningful differences between the biosimilar product and the reference product. Biosimilarity of TOFIDENCE has been demonstrated for the condition(s) of use (e.g., indication(s), dosing regimen(s)), strength(s), dosage form(s), and route(s) of administration described in its Full Prescribing Information.

WARNING: RISK OF SERIOUS INFECTIONS

See full prescribing information for complete boxed warning.

- Serious infections leading to hospitalization or death including tuberculosis (TB), bacterial, invasive fungal, viral, and other opportunistic infections have occurred in patients receiving tocilizumab products. (5.1)
- If a serious infection develops, interrupt TOFIDENCE until the infection is controlled. (5.1)
- Perform test for latent TB (except patients with COVID-19); if positive, start treatment for TB prior to starting TOFIDENCE. (5.1)
- Monitor all patients for active TB during treatment, even if initial latent TB test is negative. (5.1)

RECENT MAJOR CHANGES

Warnings and Precautions (5.6) | 11/2024

1 INDICATIONS AND USAGE

TOFIDENCE™ (tocilizumab-bavi) is an interleukin-6 (IL-6) receptor antagonist indicated for treatment of:

Rheumatoid Arthritis (RA) (1.1)

- Adult patients with moderately to severely active rheumatoid arthritis who have had an inadequate response to one or more Disease-Modifying Anti-Rheumatic Drugs (DMARDs).

Giant Cell Arteritis (GCA) (1.2)

- Adult patients with giant cell arteritis.

Polyarticular Juvenile Idiopathic Arthritis (PJIA) (1.3)

- Patients 2 years of age and older with active polyarticular juvenile idiopathic arthritis.

Systemic Juvenile Idiopathic Arthritis (SJIA) (1.4)

- Patients 2 years of age and older with active systemic juvenile idiopathic arthritis.

Coronavirus Disease 2019 (COVID-19) (1.5)

- Hospitalized adult patients with coronavirus disease 2019 (COVID-19) who are receiving systemic corticosteroids and require supplemental oxygen, non-invasive or invasive mechanical ventilation, or extracorporeal membrane oxygenation (ECMO).

2 DOSAGE AND ADMINISTRATION

For RA, pJIA and sJIA, TOFIDENCE may be used alone or in combination with methotrexate; and in RA, other non-biologic DMARDs may be used. (2)

General Administration and Dosing Information (2.1)

- RA, GCA, PJIA and SJIA- It is recommended that TOFIDENCE not be initiated in patients with an absolute neutrophil count (ANC) below 2000 per mm^3, platelet count below 100,000 per mm^3, or ALT or AST above 1.5 times the upper limit of normal (ULN). (5.3, 5.4)
- COVID-19- It is recommended that TOFIDENCE not be initiated in patients with an absolute neutrophil count (ANC) below 1000 per mm3 , platelet count below 50,000 mm3 , or ALT or AST above 10 times ULN (5.3, 5.4).
- In RA or COVID-19patients, TOFIDENCE doses exceeding 800 mg per infusion are not recommended. (2.2, 12.3)
- In GCApatients, TOFIDENCE doses exceeding 600 mg per infusion are not recommended. (2.3, 12.3)

Rheumatoid Arthritis (2.2)

Recommended Adult Intravenous Dosage:

When used in combination with non-biologic DMARDs or as monotherapy the recommended starting dose is 4 mg per kg every 4 weeks followed by an increase to 8 mg per kg every 4 weeks based on clinical response.

Giant Cell Arteritis (2.3)

Recommended Adult Intravenous Dosage:

The recommended dose is 6 mg per kg every 4 weeks in combination with a tapering course of glucocorticoids. TOFIDENCE can be used alone following discontinuation of glucocorticoids.

Polyarticular Juvenile Idiopathic Arthritis (2.4)

Recommended Intravenous PJIA Dosage Every 4 Weeks
Patients less than 30 kg weight | 10 mg per kg
Patients at or above 30 kg weight | 8 mg per kg

Systemic Juvenile Idiopathic Arthritis (2.5)

Recommended Intravenous SJIA Dosage Every 2 Weeks
Patients less than 30 kg weight | 12 mg per kg
Patients at or above 30 kg weight | 8 mg per kg

Coronavirus Disease 2019 (2.6)

The recommended dosage of TOFIDENCE for adult patients with COVID-19 is 8 mg per kg administered by a 60-minute intravenous infusion.

Administration of Intravenous Formulation (2.7)

- For patients with RA, GCA, COVID-19, PJIA, and SJIA patients at or above 30 kg, dilute to 100 mL in 0.9% Sodium Chloride Injection, USP for intravenous infusion using aseptic technique.
- For PJIA and SJIA patients less than 30 kg, dilute to 50 mL in 0.9% Sodium Chloride Injection, USP for intravenous infusion using aseptic technique.
- Administer as a single intravenous drip infusion over 1 hour; do not administer as bolus or push.

Dose Modifications (2.8)

- Recommended for management of certain dose-related laboratory changes including elevated liver enzymes, neutropenia, and thrombocytopenia.

3 DOSAGE FORMS AND STRENGTHS

Intravenous Infusion

Injection: 80 mg/4 mL (20 mg/mL), 200 mg/10 mL (20 mg/mL), 400 mg/20 mL (20 mg/mL) in single-dose vials for further dilution prior to intravenous infusion (3)

4 CONTRAINDICATIONS

- Known hypersensitivity to tocilizumab products. (4)

5 WARNINGS AND PRECAUTIONS

- Serious Infections – do not administer TOFIDENCE during an active infection, including localized infections. If a serious infection develops, interrupt TOFIDENCE until the infection is controlled. (5.1)
- Gastrointestinal (GI) perforation—use with caution in patients who may be at increased risk. (5.2)
- Hepatotoxicity- Monitor patients for signs and symptoms of hepatic injury. Modify or discontinue TOFIDENCE if abnormal liver tests persist or worsen or if clinical signs and symptoms of liver disease develop. (2.8, 5.3)
- Laboratory monitoring—recommended due to potential consequences of treatment-related changes in neutrophils, platelets, lipids, and liver function tests. (2.8, 5.4)
- Hypersensitivity reactions, including anaphylaxis and death and serious cutaneous reactions including Drug Reaction with Eosinophilia and Systemic Symptoms (DRESS) – discontinue TOFIDENCE, treat promptly, and monitor until reaction resolves (5.6)
- Live vaccines—Avoid use with TOFIDENCE. (5.9, 7.3)

6 ADVERSE REACTIONS

Most common adverse reactions (incidence of at least 5%): upper respiratory tract infections, nasopharyngitis, headache, hypertension, increased ALT. (6)

To report SUSPECTED ADVERSE REACTIONS, contact Biogen MA Inc. at 1-877-422-8360 or FDA at 1-800-FDA-1088 or www.fda.gov/medwatch

8 USE IN SPECIFIC POPULATIONS

- Pregnancy:Based on animal data, may cause fetal harm. (8.1)
- Lactation:Discontinue drug or nursing taking into consideration importance of drug to mother. (8.2)

FULL PRESCRIBING INFORMATION

WARNING: RISK OF SERIOUS INFECTIONS

Patients treated with tocilizumab products including TOFIDENCE are at increased risk for developing serious infections that may lead to hospitalization or death [see Warnings and Precautions (5.1), Adverse Reactions (6.1)]. Most patients who developed these infections were taking concomitant immunosuppressants such as methotrexate or corticosteroids.

If a serious infection develops, interrupt TOFIDENCE until the infection is controlled.

Reported infections include:

- Active tuberculosis, which may present with pulmonary or extrapulmonary disease. Patients, except those with COVID-19, should be tested for latent tuberculosis before TOFIDENCE use and during therapy. Treatment for latent infection should be initiated prior to TOFIDENCE use.
- Invasive fungal infections, including candidiasis, aspergillosis, and pneumocystis. Patients with invasive fungal infections may present with disseminated, rather than localized, disease.
- Bacterial, viral and other infections due to opportunistic pathogens.

The risks and benefits of treatment with TOFIDENCE should be carefully considered prior to initiating therapy in patients with chronic or recurrent infection.

Patients should be closely monitored for the development of signs and symptoms of infection during and after treatment with TOFIDENCE, including the possible development of tuberculosis in patients who tested negative for latent tuberculosis infection prior to initiating therapy [see Warnings and Precautions (5.1)].

1 INDICATIONS AND USAGE

1.1 Rheumatoid Arthritis (RA)

TOFIDENCE (tocilizumab-bavi) is indicated for the treatment of adult patients with moderately to severely active rheumatoid arthritis who have had an inadequate response to one or more Disease-Modifying Anti-Rheumatic Drugs (DMARDs).

1.2 Giant Cell Arteritis (GCA)

TOFIDENCE™ (tocilizumab-bavi) is indicated for the treatment of giant cell arteritis (GCA) in adult patients.

1.3 Polyarticular Juvenile Idiopathic Arthritis (PJIA)

TOFIDENCE™ (tocilizumab-bavi) is indicated for the treatment of active polyarticular juvenile idiopathic arthritis in patients 2 years of age and older.

1.4 Systemic Juvenile Idiopathic Arthritis (SJIA)

TOFIDENCE™ (tocilizumab-bavi) is indicated for the treatment of active systemic juvenile idiopathic arthritis in patients 2 years of age and older.

1.5 Coronavirus Disease 2019 (COVID-19)

TOFIDENCE™ (tocilizumab-bavi) is indicated for the treatment of coronavirus disease 2019 (COVID-19) in hospitalized adult patients who are receiving systemic corticosteroids and require supplemental oxygen, non-invasive or invasive mechanical ventilation, or extracorporeal membrane oxygenation (ECMO).

2 DOSAGE AND ADMINISTRATION

2.1 General Considerations for Administration

Not Recommended for Concomitant Use with Biological DMARDs

Tocilizumab products have not been studied in combination with biological DMARDs such as TNF antagonists, IL-1R antagonists, anti-CD20 monoclonal antibodies and selective co-stimulation modulators because of the possibility of increased immunosuppression and increased risk of infection. Avoid using TOFIDENCE with biological DMARDs.

Baseline Laboratory Evaluation Prior to Treatment

Obtain and assess baseline complete blood count (CBC) and liver function tests prior to treatment.

- RA, GCA, PJIA and SJIA – It is recommended that TOFIDENCE not be initiated in patients with an absolute neutrophil count (ANC) below 2000 per mm^3, platelet count below 100,000 per mm^3, or ALT or AST above 1.5 times the upper limit of normal (ULN) [see Warnings and Precautions (5.3, 5.4)] .
- COVID-19- It is recommended that TOFIDENCE not be initiated in patients with an absolute neutrophil count (ANC) below 1000 per mm3 , platelet count below 50,000 mm3 , or ALT or AST above 10 times ULN [see Warnings and Precautions (5.3, 5.4)]

2.2 Recommended Dosage for Rheumatoid Arthritis

TOFIDENCE may be used as monotherapy or concomitantly with methotrexate or other non-biologic DMARDs as an intravenous infusion.

Recommended Intravenous Dosage Regimen:

The recommended dosage of TOFIDENCE for adult patients given as a 60-minute single intravenous drip infusion is 4 mg per kg every 4 weeks followed by an increase to 8 mg per kg every 4 weeks based on clinical response.

- Reduction of dose from 8 mg per kg to 4 mg per kg is recommended for management of certain dose-related laboratory changes including elevated liver enzymes, neutropenia, and thrombocytopenia [see Dosage and Administration (2.8), Warnings and Precautions (5.3, 5.4), and Adverse Reactions (6.1)].
- Doses exceeding 800 mg per infusion are not recommended in RA patients [see Clinical Pharmacology (12.3)].

When transitioning from intravenous therapy with TOFIDENCE to subcutaneous therapy with another tocilizumab product, administer the first subcutaneous dose instead of the next scheduled intravenous dose.

Interruption of dose is recommended for management of certain dose-related laboratory changes including elevated liver enzymes, neutropenia, and thrombocytopenia [see Dosage and Administration (2.8)and Warnings and Precautions (5.3, 5.4).

2.3 Recommended Dosage for Giant Cell Arteritis

Recommended Intravenous Dosage Regimen:

The recommended dosage of TOFIDENCE for adult patients given as a 60-minute single intravenous drip infusion is 6 mg per kg every 4 weeks in combination with tapering course of glucocorticoids.

TOFIDENCE can be used alone following discontinuation of glucocorticoids.

- Interruption of dosing may be needed for management of dose-related laboratory abnormalities including elevated liver enzymes, neutropenia, and thrombocytopenia [see Dosage and Administration (2.8)].
- Doses exceeding 600 mg per infusion are not recommended in GCA patients [see Clinical Pharmacology (12.3)].

When transitioning from intravenous therapy with TOFIDENCE to subcutaneous therapy with another tocilizumab product, administer the first subcutaneous dose instead of the next scheduled intravenous dose.

2.4 Recommended Dosage for Polyarticular Juvenile Idiopathic Arthritis

TOFIDENCE may be used as an intravenous infusion alone or in combination with methotrexate. Do not change dose based solely on a single visit body weight measurement, as weight may fluctuate.

Recommended Intravenous Dosage Regimen:

The recommended dosage of TOFIDENCE for PJIA patients given once every 4 weeks as a 60-minute single intravenous drip infusion is:

Recommended Intravenous PJIA Dosage Every 4 Weeks
Patients less than 30 kg weight | 10 mg per kg
Patients at or above 30 kg weight | 8 mg per kg

When transitioning from intravenous therapy with TOFIDENCE to subcutaneous therapy with another tocilizumab product, administer the first subcutaneous dose instead of the next scheduled intravenous dose.

Interruption of dosing may be needed for management of dose-related laboratory abnormalities including elevated liver enzymes, neutropenia, and thrombocytopenia [see Dosage and Administration (2.8)].

2.5 Recommended Dosage for Systemic Juvenile Idiopathic Arthritis

TOFIDENCE may be used as an intravenous infusion or in combination with methotrexate. Do not change a dose based solely on a single visit body weight measurement, as weight may fluctuate.

Recommended Intravenous Dosage Regimen:

The recommended dose of TOFIDENCE for SJIA patients given once every 2 weeks as a 60-minute single intravenous drip infusion is:

Recommended Intravenous SJIA Dosage Every 2 Weeks
Patients less than 30 kg weight | 12 mg per kg
Patients at or above 30 kg weight | 8 mg per kg

When transitioning from intravenous therapy with TOFIDENCE to subcutaneous therapy with another tocilizumab product, administer the first subcutaneous dose instead of the next scheduled intravenous dose.

Interruption of dosing may be needed for management of dose-related laboratory abnormalities including elevated liver enzymes, neutropenia, and thrombocytopenia [see Dosage and Administration (2.8)].

2.6 Coronavirus Disease 2019 (COVID-19)

Administer TOFIDENCE by intravenous infusion only.

The recommended dosage of TOFIDENCE for treatment of adult patients with COVID-19 is 8 mg per kg administered as a single 60-minute intravenous infusion. If clinical signs or symptoms worsen or do not improve after the first dose, one additional infusion of TOFIDENCE may be administered at least 8 hours after the initial infusion.

- Doses exceeding 800 mg per infusion are not recommended in patients with COVID-19.

2.7 Preparation and Administration Instructions for Intravenous Infusion

TOFIDENCE for intravenous infusion should be diluted by a healthcare professional using aseptic technique as follows:

- Use a sterile needle and syringe to prepare TOFIDENCE.
- Patients less than 30 kg:use a 50 mLinfusion bag or bottle of 0.9% Sodium Chloride Injection, USP, and then follow steps 1 and 2 below.
- Patients at or above 30 kg weight:use a 100 mLinfusion bag or bottle, and then follow steps 1 and 2 below.
- Step 1. Withdraw a volume of 0.9% Sodium Chloride Injection, USP, equal to the volume of the TOFIDENCE injection required for the patient's dose from the infusion bag or bottle [see Dosage and Administration (2.2, 2.4, 2.5)].

For Intravenous Use: Volume of TOFIDENCE Injection per kg of Body Weight
Dosage | Indication | Volume of TOFIDENCE injection per kg of body weight
4 mg/kg | Adult RA | 0.2 mL/kg
6 mg/kg | Adult GCA | 0.3 mL/kg
8 mg/kg | Adult RA Adult COVID-19 SJIA and PJIA (greater than or equal to 30 kg of body weight) | 0.4 mL/kg
10 mg/kg | PJIA (less than 30 kg of body weight) | 0.5 mL/kg
12 mg/kg | SJIA (less than 30 kg of body weight) | 0.6 mL/kg

- Step 2. Withdraw the amount of TOFIDENCE for intravenous infusion from the vial(s) and add slowly into the 0.9% Sodium Chloride Injection, USP infusion bag or bottle. To mix the solution, gently invert the bag to avoid foaming.
- The fully diluted TOFIDENCE solutions for infusion using 0.9% Sodium Chloride Injection, USP may be stored refrigerated at 36°F to 46°F (2°C to 8°C) for up to 24 hours or room temperature at 68°F to 77°F (20°C to 25°C) for up to 12 hours and should be protected from light.
- TOFIDENCE solutions do not contain preservatives; therefore, unused product remaining in the vials should not be used.
- Allow the fully diluted TOFIDENCE solution to reach room temperature prior to infusion.
- The infusion should be administered over 60 minutes, and must be administered with an infusion set. Do not administer as an intravenous push or bolus.
- TOFIDENCE should not be infused concomitantly in the same intravenous line with other drugs. No physical or biochemical compatibility studies have been conducted to evaluate the co-administration of TOFIDENCE with other drugs.
- Parenteral drug products should be inspected visually for particulate matter and discoloration prior to administration, whenever solution and container permit. If particulates and discolorations are noted, the product should not be used.
- Fully diluted TOFIDENCE solutions are compatible with infusion bags and/or infusion sets with the following materials: polypropylene, polyethylene, polyolefin, polyvinyl chloride, polyethersulfone, polyurethane, nylon and stainless steel.

2.8 Dosage Modifications due to Serious Infections or Laboratory Abnormalities

Serious Infections

Hold TOFIDENCE treatment if a patient develops a serious infection until the infection is controlled.

Laboratory Abnormalities

Rheumatoid Arthritis and Giant Cell Arteritis

Liver Enzyme Abnormalities [see Warnings and Precautions (5.3, 5.4)]
Lab Value | Recommendation for RA | Recommendation for GCA
Greater than 1 to 3× ULN | Dose modify concomitant DMARDs if appropriate. For persistent increases in this range:; - For patients receiving intravenous TOFIDENCE, reduce dose to 4 mg per kg or hold TOFIDENCE until ALT or AST have normalized. | Dose modify immunomodulatory agents if appropriate For persistent increases in this range:; - For patients receiving intravenous TOFIDENCE, hold TOFIDENCE until ALT or AST have normalized.
Greater than 3 to 5× ULN (confirmed by repeat testing) | Hold TOFIDENCE dosing until less than 3× ULN and follow recommendations above for greater than 1 to 3× ULN. For persistent increases greater than 3× ULN, discontinue TOFIDENCE. | Hold TOFIDENCE dosing until less than 3× ULN and follow recommendations above for greater than 1 to 3× ULN. For persistent increases greater than 3× ULN, discontinue TOFIDENCE.
Greater than 5× ULN | Discontinue TOFIDENCE. | Discontinue TOFIDENCE.

Low Absolute Neutrophil Count (ANC) [see Warnings and Precautions (5.4)]
Lab Value (cells per mm^3) | Recommendation for RA | Recommendation for GCA
ANC greater than 1000 | Maintain dose. | Maintain dose.
ANC 500 to 1000 | Hold TOFIDENCE dosing. When ANC greater than 1000 cells per mm3:; - For patients receiving intravenous TOFIDENCE, resume TOFIDENCE at 4 mg per kg and increase to 8 mg per kg as clinically appropriate. | Hold TOFIDENCE dosing. When ANC greater than 1000 cells per mm^3:; - For patients receiving intravenous TOFIDENCE, resume TOFIDENCE at 6 mg per kg.
ANC less than 500 | Discontinue TOFIDENCE. | Discontinue TOFIDENCE.

Low Platelet Count [see Warnings and Precautions (5.4)]
Lab Value (cells per mm^3) | Recommendation for RA | Recommendation for GCA
50,000 to 100,000 | Hold TOFIDENCE dosing. When platelet count is greater than 100,000 cells per mm^3:; - For patients receiving intravenous TOFIDENCE, resume TOFIDENCE at 4 mg per kg and increase to 8 mg per kg as clinically appropriate. | Hold TOFIDENCE dosing When platelet count is greater than 100,000 cells per mm^3:; - For patients receiving intravenous TOFIDENCE, resume TOFIDENCE at 6 mg per kg.
Less than 50,000 | Discontinue TOFIDENCE. | Discontinue TOFIDENCE.

Polyarticular and Systemic Juvenile Idiopathic Arthritis

Dose reduction of tocilizumab products has not been studied in the PJIA and SJIA populations. Dose interruptions of TOFIDENCE are recommended for liver enzyme abnormalities, low neutrophil counts, and low platelet counts in patients with PJIA and SJIA at levels similar to what is outlined above for patients with RA and GCA. If appropriate, dose modify or stop concomitant methotrexate and/or other medications and hold TOFIDENCE dosing until the clinical situation has been evaluated. In PJIA and SJIA the decision to discontinue TOFIDENCE for a laboratory abnormality should be based upon the medical assessment of the individual patient.

3 DOSAGE FORMS AND STRENGTHS

Intravenous Infusion

Injection: 80 mg/4 mL, 200 mg/10 mL, 400 mg/20 mL as a clear to opalescent, colorless to light yellow solution in 20 mg/mL single-dose vials for further dilution prior to intravenous infusion.

4 CONTRAINDICATIONS

TOFIDENCE is contraindicated in patients with known hypersensitivity to tocilizumab products [see Warnings and Precautions (5.6)].

5 WARNINGS AND PRECAUTIONS

5.1 Serious Infections

Serious and sometimes fatal infections due to bacterial, mycobacterial, invasive fungal, viral, protozoal, or other opportunistic pathogens have been reported in patients receiving immunosuppressive agents including tocilizumab products. The most common serious infections included pneumonia, urinary tract infection, cellulitis, herpes zoster, gastroenteritis, diverticulitis, sepsis and bacterial arthritis [see Adverse Reactions (6.1)]. Among opportunistic infections, tuberculosis, cryptococcus, aspergillosis, candidiasis, and pneumocystosis were reported with tocilizumab products. Other serious infections, not reported in clinical studies, may also occur (e.g., histoplasmosis, coccidioidomycosis, listeriosis). Patients have presented with disseminated rather than localized disease, and were often taking concomitant immunosuppressants such as methotrexate or corticosteroids which in addition to rheumatoid arthritis may predispose them to infections.

Do not administer TOFIDENCE in patients with an active infection, including localized infections. The risks and benefits of treatment should be considered prior to initiating TOFIDENCE in patients:

- with chronic or recurrent infection;
- who have been exposed to tuberculosis;
- with a history of serious or an opportunistic infection;
- who have resided or traveled in areas of endemic tuberculosis or endemic mycoses; or
- with underlying conditions that may predispose them to infection.

Closely monitor patients for the development of signs and symptoms of infection during and after treatment with TOFIDENCE, as signs and symptoms of acute inflammation may be lessened due to suppression of the acute phase reactants [see Dosage and Administration (2.1), Adverse Reactions (6.1), and Patient Counseling Information (17)].

Hold TOFIDENCE if a patient develops a serious infection, an opportunistic infection, or sepsis. A patient who develops a new infection during treatment with TOFIDENCE should undergo a prompt and complete diagnostic workup appropriate for an immunocompromised patient, initiate appropriate antimicrobial therapy, and closely monitor the patient.

COVID-19

In patients with COVID-19, monitor for signs and symptoms of new infections during and after treatment with TOFIDENCE. There is limited information regarding the use of tocilizumab products in patients with COVID-19 and concomitant active serious infections. The risks and benefits of treatment with TOFIDENCE in COVID-19 patients with other concurrent infections should be considered.

Tuberculosis

Evaluate patients for tuberculosis risk factors and test for latent infection prior to initiating TOFIDENCE. In patients with COVID-19, testing for latent infection is not necessary prior to initiating treatment with TOFIDENCE.

Consider anti-tuberculosis therapy prior to initiation of TOFIDENCE in patients with a past history of latent or active tuberculosis in whom an adequate course of treatment cannot be confirmed, and for patients with a negative test for latent tuberculosis but having risk factors for tuberculosis infection. Consultation with a physician with expertise in the treatment of tuberculosis is recommended to aid in the decision whether initiating anti-tuberculosis therapy is appropriate for an individual patient.

Closely monitor patients for the development of signs and symptoms of tuberculosis including patients who tested negative for latent tuberculosis infection prior to initiating therapy.

The incidence of tuberculosis in worldwide clinical development programs is 0.1%. Patients with latent tuberculosis should be treated with standard antimycobacterial therapy before initiating TOFIDENCE.

Viral Reactivation

Viral reactivation has been reported with immunosuppressive biologic therapies and cases of herpes zoster exacerbation were observed in clinical studies with tocilizumab. No cases of Hepatitis B reactivation were observed in the trials; however patients who screened positive for hepatitis were excluded.

5.2 Gastrointestinal Perforations

Events of gastrointestinal perforation have been reported in clinical trials, primarily as complications of diverticulitis in patients treated with tocilizumab. Use TOFIDENCE with caution in patients who may be at increased risk for gastrointestinal perforation. Promptly evaluate patients presenting with fever, new onset abdominal symptoms, and a change in bowel habits for early identification of gastrointestinal perforation [see Adverse Reactions (6.1)].

5.3 Hepatotoxicity

Serious cases of hepatic injury have been observed in patients taking intravenous tocilizumab products. Some of these cases have resulted in liver transplant or death. Time to onset for cases ranged from months to years after treatment initiation with tocilizumab products. While most cases presented with marked elevations of transaminases (> 5 times ULN), some cases presented with signs or symptoms of liver dysfunction and only mildly elevated transaminases.

During randomized controlled studies, treatment with tocilizumab was associated with a higher incidence of transaminase elevations [see Adverse Reactions (6.1, 6.3, 6.4)]. Increased frequency and magnitude of these elevations was observed when potentially hepatotoxic drugs (e.g., MTX) were used in combination with tocilizumab.

For RA and GCA patients, obtain a liver test panel (serum alanine aminotransferase [ALT], aspartate aminotransferase [AST], alkaline phosphatase, and total bilirubin) before initiating TOFIDENCE, every 4 to 8 weeks after start of therapy for the first 6 months of treatment and every 3 months thereafter. It is not recommended to initiate TOFIDENCE treatment in RA or GCA patients with elevated transaminases ALT or AST greater than 1.5× ULN. In patients who develop elevated ALT or AST greater than 5× ULN, discontinue TOFIDENCE. For recommended modifications based upon increase in transaminases [see Dosage and Administration (2.8)].

Patients hospitalized with COVID-19 may have elevated ALT or AST levels. Multi-organ failure with involvement of the liver is recognized as a complication of severe COVID-19. The decision to administer TOFIDENCE should balance the potential benefit of treating COVID-19 against the potential risks of acute treatment with TOFIDENCE. It is not recommended to initiate TOFIDENCE treatment in COVID-19 patients with elevated ALT or AST above 10 × ULN. Monitor ALT and AST during treatment.

Measure liver tests promptly in patients who report symptoms that may indicate liver injury, such as fatigue, anorexia, right upper abdominal discomfort, dark urine or jaundice. In this clinical context, if the patient is found to have abnormal liver tests (e.g., ALT greater than three times the upper limit of the reference range, serum total bilirubin greater than two times the upper limit of the reference range), TOFIDENCE treatment should be interrupted and investigation done to establish the probable cause. TOFIDENCE should only be restarted in patients with another explanation for the liver test abnormalities after normalization of the liver tests.

A similar pattern of liver enzyme elevation is noted with tocilizumab products treatment in the PJIA and SJIA populations. Monitor liver test panel at the time of the second administration and thereafter every 4 to 8 weeks for PJIA and every 2 to 4 weeks for SJIA.

5.4 Changes in Laboratory Parameters

Patients with Rheumatoid Arthritis, Giant Cell Arteritis and Coronavirus Disease 2019

Neutropenia

Treatment with tocilizumab products was associated with a higher incidence of neutropenia. Infections have been uncommonly reported in association with treatment-related neutropenia in long-term extension studies and postmarketing clinical experience.

– It is not recommended to initiate TOFIDENCE treatment in RA and GCA patients with a low neutrophil count, i.e., absolute neutrophil count (ANC) less than 2000 per mm^3. In patients who develop an absolute neutrophil count less than 500 per mm^3treatment is not recommended.

– Monitor neutrophils 4 to 8 weeks after start of therapy and every 3 months thereafter [see Clinical Pharmacology (12.2)]. For recommended modifications based on ANC results see Dosage and Administration (2.8).

– It is not recommended to initiate TOFIDENCE treatment in COVID-19 patients with an ANC less than 1000 per mm^3. Neutrophils should be monitored.

Thrombocytopenia

Treatment with tocilizumab products was associated with a reduction in platelet counts. Treatment-related reduction in platelets was not associated with serious bleeding events in clinical trials [see Adverse Reactions (6.1)].

– It is not recommended to initiate TOFIDENCE treatment in RA and GCA patients with a platelet count below 100,000 per mm^3. In patients who develop a platelet count less than 50,000 per mm^3treatment is not recommended.

– Monitor platelets 4 to 8 weeks after start of therapy and every 3 months thereafter. For recommended modifications based on platelet counts see Dosage and Administration (2.8).

– In COVID-19 patients with a platelet count less than 50,000 per mm^3, treatment is not recommended. Platelets should be monitored.

Elevated Liver Enzymes

Refer to 5.3 Hepatotoxicity. For recommended modifications see Dosage and Administration (2.8).

Lipid Abnormalities

Treatment with tocilizumab products was associated with increases in lipid parameters such as total cholesterol, triglycerides, LDL cholesterol, and/or HDL cholesterol [see Adverse Reactions (6.1)].

– Assess lipid parameters approximately 4 to 8 weeks following initiation of TOFIDENCE therapy.

– Subsequently, manage patients according to clinical guidelines [e.g., National Cholesterol Educational Program (NCEP)] for the management of hyperlipidemia.

Patients with Polyarticular and Systemic Juvenile Idiopathic Arthritis

A similar pattern of liver enzyme elevation, low neutrophil count, low platelet count and lipid elevations is noted with tocilizumab products treatment in the PJIA and SJIA populations. Monitor neutrophils, platelets, ALT and AST at the time of the second administration and thereafter every 4 to 8 weeks for PJIA and every 2 to 4 weeks for SJIA. Monitor lipids as above for approved adult indications [see Dosage and Administration (2.8)].

5.5 Immunosuppression

The impact of treatment with tocilizumab products on the development of malignancies is not known but malignancies were observed in clinical studies [see Adverse Reactions (6.1)]. TOFIDENCE is an immunosuppressant, and treatment with immunosuppressants may result in an increased risk of malignancies.

5.6 Hypersensitivity Reactions, Including Anaphylaxis

Hypersensitivity reactions, including anaphylaxis, have been reported in association with tocilizumab products and anaphylactic events with a fatal outcome have been reported with intravenous infusion of tocilizumab products. Anaphylaxis and other hypersensitivity reactions that required treatment discontinuation were reported in 0.1% (3 out of 2644) of patients in the 6-month controlled trials of intravenous tocilizumab and 0.2% (8 out of 4009) of patients in the intravenous all-exposure RA population. In the SJIA controlled trial with intravenous tocilizumab, 1 out of 112 patients (0.9%) experienced hypersensitivity reactions that required treatment discontinuation. In the PJIA controlled trial with intravenous tocilizumab 0 out of 188 patients (0%) in the tocilizumab all-exposure population experienced hypersensitivity reactions that required treatment discontinuation. Reactions that required treatment discontinuation included generalized erythema, rash, and urticaria.

In the postmarketing setting, events of hypersensitivity reactions, including anaphylaxis and death have occurred in patients treated with a range of doses of intravenous tocilizumab products, with or without concomitant therapies. Events have occurred in patients who received premedication. Hypersensitivity, including anaphylaxis events, have occurred both with and without previous hypersensitivity reactions and as early as the first infusion of tocilizumab products [see Adverse Reactions (6.6)]. In addition, serious cutaneous reactions, including Drug Reaction with Eosinophilia and Systemic Symptoms (DRESS), have been reported in patients with autoinflammatory conditions treated with tocilizumab products.

TOFIDENCE for intravenous use should only be infused by a healthcare professional with appropriate medical support to manage anaphylaxis. If a hypersensitivity reaction occurs, immediately discontinue TOFIDENCE, treat promptly and monitor until signs and symptoms resolve.

5.7 Demyelinating Disorders

The impact of treatment with tocilizumab products on demyelinating disorders is not known, but multiple sclerosis and chronic inflammatory demyelinating polyneuropathy were reported rarely in RA clinical studies. Monitor patients for signs and symptoms potentially indicative of demyelinating disorders. Prescribers should exercise caution in considering the use of TOFIDENCE in patients with preexisting or recent onset demyelinating disorders.

5.8 Active Hepatic Disease and Hepatic Impairment

Treatment with TOFIDENCE is not recommended in patients with active hepatic disease or hepatic impairment [see Adverse Reactions (6.1), Use in Specific Populations (8.6)].

5.9 Vaccinations

Avoid use of live vaccines concurrently with TOFIDENCE as clinical safety has not been established. No data are available on the secondary transmission of infection from persons receiving live vaccines to patients receiving tocilizumab products.

No data are available on the effectiveness of vaccination in patients receiving tocilizumab products. Because IL-6 inhibition may interfere with the normal immune response to new antigens, it is recommended that all patients, particularly pediatric or elderly patients, if possible, be brought up to date with all immunizations in agreement with current immunization guidelines prior to initiating TOFIDENCE therapy. The interval between live vaccinations and initiation of TOFIDENCE therapy should be in accordance with current vaccination guidelines regarding immunosuppressive agents.

6 ADVERSE REACTIONS

The following serious adverse reactions are described elsewhere in labeling:

- Serious Infections [see Warnings and Precautions (5.1)]
- Gastrointestinal Perforations [see Warnings and Precautions (5.2)]
- Laboratory Parameters [see Warnings and Precautions (5.4)]
- Immunosuppression [see Warnings and Precautions (5.5)]
- Hypersensitivity Reactions, Including Anaphylaxis [see Warnings and Precautions (5.6)]
- Demyelinating Disorders [see Warnings and Precautions (5.7)]
- Active Hepatic Disease and Hepatic Impairment [see Warnings and Precautions (5.8)]

Because clinical studies are conducted under widely varying conditions, adverse reaction rates observed in the clinical studies of a drug cannot be directly compared to rates in the clinical studies of another drug and may not predict the rates observed in a broader patient population in clinical practice.

6.1 Clinical Trials Experience in Rheumatoid Arthritis Patients Treated with Intravenous Tocilizumab (Tocilizumab-IV)

The tocilizumab-IV data in rheumatoid arthritis (RA) includes 5 double-blind, controlled, multicenter studies. In these studies, patients received doses of tocilizumab-IV 8 mg per kg monotherapy (288 patients), tocilizumab-IV 8 mg per kg in combination with DMARDs (including methotrexate) (1582 patients), or tocilizumab-IV 4 mg per kg in combination with methotrexate (774 patients).

The all exposure population includes all patients in registration studies who received at least one dose of tocilizumab-IV. Of the 4009 patients in this population, 3577 received treatment for at least 6 months, 3309 for at least one year; 2954 received treatment for at least 2 years and 2189 for 3 years.

All patients in these studies had moderately to severely active rheumatoid arthritis. The study population had a mean age of 52 years, 82% were female and 74% were Caucasian.

The most common serious adverse reactions were serious infections [see Warnings and Precautions (5.1)]. The most commonly reported adverse reactions in controlled studies up to 24 weeks (occurring in at least 5% of patients treated with tocilizumab-IV monotherapy or in combination with DMARDs) were upper respiratory tract infections, nasopharyngitis, headache, hypertension and increased ALT.

The proportion of patients who discontinued treatment due to any adverse reactions during the double-blind, placebo-controlled studies was 5% for patients taking tocilizumab-IV and 3% for placebo-treated patients. The most common adverse reactions that required discontinuation of tocilizumab-IV were increased hepatic transaminase values (per protocol requirement) and serious infections.

Overall Infections

In the 24 week, controlled clinical studies, the rate of infections in the tocilizumab-IV monotherapy group was 119 events per 100 patient-years and was similar in the methotrexate monotherapy group. The rate of infections in the 4 mg per kg and 8 mg per kg tocilizumab-IV plus DMARD group was 133 and 127 events per 100 patient-years, respectively, compared to 112 events per 100 patient-years in the placebo plus DMARD group. The most commonly reported infections (5% to 8% of patients) were upper respiratory tract infections and nasopharyngitis.

The overall rate of infections with tocilizumab-IV in the all exposure population remained consistent with rates in the controlled periods of the studies.

Serious Infections

In the 24 week, controlled clinical studies, the rate of serious infections in the tocilizumab-IV monotherapy group was 3.6 per 100 patient-years compared to 1.5 per 100 patient-years in the methotrexate group. The rate of serious infections in the 4 mg per kg and 8 mg per kg tocilizumab-IV plus DMARD group was 4.4 and 5.3 events per 100 patient-years, respectively, compared to 3.9 events per 100 patient-years in the placebo plus DMARD group.

In the all-exposure population, the overall rate of serious infections remained consistent with rates in the controlled periods of the studies. The most common serious infections included pneumonia, urinary tract infection, cellulitis, herpes zoster, gastroenteritis, diverticulitis, sepsis and bacterial arthritis. Cases of opportunistic infections have been reported [see Warnings and Precautions (5.1)].

In the cardiovascular outcomes Study WA25204, the rate of serious infections in the tocilizumab 8 mg/kg IV every 4 weeks group, with or without DMARD, was 4.5 per 100 patient-years, and the rate in the etanercept 50 mg weekly SC group, with or without DMARD, was 3.2 per 100 patient-years [see Clinical Studies (14.1)].

Gastrointestinal Perforations

During the 24 week, controlled clinical trials, the overall rate of gastrointestinal perforation was 0.26 events per 100 patient-years with tocilizumab-IV therapy.

In the all-exposure population, the overall rate of gastrointestinal perforation remained consistent with rates in the controlled periods of the studies. Reports of gastrointestinal perforation were primarily reported as complications of diverticulitis including generalized purulent peritonitis, lower GI perforation, fistula and abscess. Most patients who developed gastrointestinal perforations were taking concomitant nonsteroidal anti-inflammatory medications (NSAIDs), corticosteroids, or methotrexate [see Warnings and Precautions (5.2)]. The relative contribution of these concomitant medications versus tocilizumab-IV to the development of GI perforations is not known.

Infusion Reactions

In the 24 week, controlled clinical studies, adverse events associated with the infusion (occurring during or within 24 hours of the start of infusion) were reported in 8% and 7% of patients in the 4 mg per kg and 8 mg per kg tocilizumab-IV plus DMARD group, respectively, compared to 5% of patients in the placebo plus DMARD group. The most frequently reported event on the 4 mg per kg and 8 mg per kg dose during the infusion was hypertension (1% for both doses), while the most frequently reported event occurring within 24 hours of finishing an infusion were headache (1% for both doses) and skin reactions (1% for both doses), including rash, pruritus and urticaria. These events were not treatment limiting.

Anaphylaxis

Hypersensitivity reactions requiring treatment discontinuation, including anaphylaxis, associated with tocilizumab-IV were reported in 0.1% (3 out of 2644) in the 24 week, controlled trials and in 0.2% (8 out of 4009) in the all-exposure population. These reactions were generally observed during the second to fourth infusion of tocilizumab-IV. Appropriate medical treatment should be available for immediate use in the event of a serious hypersensitivity reaction [see Warnings and Precautions (5.6)].

Laboratory Abnormalities

Neutropenia

In the 24 week, controlled clinical studies, decreases in neutrophil counts below 1000 per mm^3occurred in 1.8% and 3.4% of patients in the 4 mg per kg and 8 mg per kg tocilizumab-IV plus DMARD group, respectively, compared to 0.1% of patients in the placebo plus DMARD group. Approximately half of the instances of ANC below 1000 per mm^3occurred within 8 weeks of starting therapy. Decreases in neutrophil counts below 500 per mm^3occurred in 0.4% and 0.3% of patients in the 4 mg per kg and 8 mg per kg tocilizumab-IV plus DMARD, respectively, compared to 0.1% of patients in the placebo plus DMARD group. There was no clear relationship between decreases in neutrophils below 1000 per mm^3and the occurrence of serious infections.

In the all-exposure population, the pattern and incidence of decreases in neutrophil counts remained consistent with what was seen in the 24 week controlled clinical studies [see Warnings and Precautions (5.4)].

Thrombocytopenia

In the 24 week, controlled clinical studies, decreases in platelet counts below 100,000 per mm^3occurred in 1.3% and 1.7% of patients on 4 mg per kg and 8 mg per kg tocilizumab-IV plus DMARD, respectively, compared to 0.5% of patients on placebo plus DMARD, without associated bleeding events.

In the all-exposure population, the pattern and incidence of decreases in platelet counts remained consistent with what was seen in the 24 week controlled clinical studies [see Warnings and Precautions (5.4)].

Elevated Liver Enzymes

Liver enzyme abnormalities are summarized in Table 1. In patients experiencing liver enzyme elevation, modification of treatment regimen, such as reduction in the dose of concomitant DMARD, interruption of tocilizumab-IV, or reduction in tocilizumab-IV dose, resulted in decrease or normalization of liver enzymes [see Dosage and Administration (2.8)]. These elevations were not associated with clinically relevant increases in direct bilirubin, nor were they associated with clinical evidence of hepatitis or hepatic insufficiency [see Warnings and Precautions (5.3, 5.4)].

Table 1 Incidence of Liver Enzyme Abnormalities in the 24 Week Controlled Period of Studies I to V [For a description of these studies, see Section 14, Clinical Studies.]
 | Tocilizumab 8 mg per kg MONOTHERAPY | Methotrexate | Tocilizumab 4 mg per kg + DMARDs | Tocilizumab 8 mg per kg + DMARDs | Placebo + DMARDs
 | N = 288 (%) | N = 284 (%) | N = 774 (%) | N = 1582 (%) | N = 1170 (%)
AST (U/L)
> ULN to 3× ULN | 22 | 26 | 34 | 41 | 17
> 3× ULN to 5× ULN | 0.3 | 2 | 1 | 2 | 0.3
> 5× ULN | 0.7 | 0.4 | 0.1 | 0.2 | < 0.1
ALT (U/L)
> ULN to 3× ULN | 36 | 33 | 45 | 48 | 23
> 3× ULN to 5× ULN | 1 | 4 | 5 | 5 | 1
> 5× ULN | 0.7 | 1 | 1.3 | 1.5 | 0.3
ULN = Upper Limit of Normal

In the all-exposure population, the elevations in ALT and AST remained consistent with what was seen in the 24 week, controlled clinical trials.

In Study WA25204, of the 1538 patients with moderate to severe RA [see Clinical Studies (14.1)] and treated with tocilizumab, elevations in ALT or AST >3 × ULN occurred in 5.3% and 2.2% patients, respectively. One serious event of drug induced hepatitis with hyperbilirubinemia was reported in association with tocilizumab.

Lipids

Elevations in lipid parameters (total cholesterol, LDL, HDL, triglycerides) were first assessed at 6 weeks following initiation of tocilizumab-IV in the controlled 24 week clinical trials. Increases were observed at this time point and remained stable thereafter. Increases in triglycerides to levels above 500 mg per dL were rarely observed. Changes in other lipid parameters from baseline to week 24 were evaluated and are summarized below:

- Mean LDL increased by 13 mg per dL in the tocilizumab 4 mg per kg+DMARD arm, 20 mg per dL in the tocilizumab 8 mg per kg+DMARD, and 25 mg per dL in tocilizumab 8 mg per kg monotherapy.
- Mean HDL increased by 3 mg per dL in the tocilizumab 4 mg per kg+DMARD arm, 5 mg per dL in the tocilizumab 8 mg per kg+DMARD, and 4 mg per dL in tocilizumab 8 mg per kg monotherapy.
- Mean LDL/HDL ratio increased by an average of 0.14 in the tocilizumab 4 mg per kg+DMARD arm, 0.15 in the tocilizumab 8 mg per kg+DMARD, and 0.26 in tocilizumab 8 mg per kg monotherapy.
- ApoB/ApoA1 ratios were essentially unchanged in tocilizumab-treated patients.

Elevated lipids responded to lipid lowering agents.

In the all-exposure population, the elevations in lipid parameters remained consistent with what was seen in the 24 week, controlled clinical trials.

Immunogenicity

The observed incidence of anti-drug antibodies is highly dependent on the sensitivity and specificity of the assay. Differences in assay methods preclude meaningful comparisons of the incidence of anti-drug antibodies in the studies described below with the incidence of anti-drug antibodies in other studies, including those of tocilizumab or of other tocilizumab products.

In the 24 week, controlled clinical studies, a total of 2876 patients have been tested for anti-tocilizumab antibodies. Forty-six patients (2%) developed positive anti-tocilizumab antibodies, of whom 5 had an associated, medically significant, hypersensitivity reaction leading to withdrawal. Thirty patients (1%) developed neutralizing antibodies.

Malignancies

During the 24 week, controlled period of the studies, 15 malignancies were diagnosed in patients receiving tocilizumab-IV, compared to 8 malignancies in patients in the control groups. Exposure-adjusted incidence was similar in the tocilizumab-IV groups (1.32 events per 100 patient-years) and in the placebo plus DMARD group (1.37 events per 100 patient-years).

In the all-exposure population, the rate of malignancies remained consistent with the rate observed in the 24 week, controlled period [see Warnings and Precautions (5.5)].

Other Adverse Reactions

Adverse reactions occurring in 2% or more of patients on 4 or 8 mg per kg tocilizumab-IV plus DMARD and at least 1% greater than that observed in patients on placebo plus DMARD are summarized in Table 2 .

Table 2 Adverse Reactions Occurring in at Least 2% or More of Patients on 4 or 8 mg per kg Tocilizumab plus DMARD and at Least 1% Greater Than That Observed in Patients on Placebo plus DMARD
24 Week Phase 3 Controlled Study Population
Preferred Term | Tocilizumab 8 mg per kg MONOTHERAPY | Methotrexate | Tocilizumab 4 mg per kg + DMARDs | Tocilizumab 8 mg per kg + DMARDs | Placebo + DMARDs
Preferred Term | N = 288 (%) | N = 284 (%) | N = 774 (%) | N = 1582 (%) | N =1170 (%)
Upper Respiratory Tract Infection | 7 | 5 | 6 | 8 | 6
Nasopharyngitis | 7 | 6 | 4 | 6 | 4
Headache | 7 | 2 | 6 | 5 | 3
Hypertension | 6 | 2 | 4 | 4 | 3
ALT increased | 6 | 4 | 3 | 3 | 1
Dizziness | 3 | 1 | 2 | 3 | 2
Bronchitis | 3 | 2 | 4 | 3 | 3
Rash | 2 | 1 | 4 | 3 | 1
Mouth Ulceration | 2 | 2 | 1 | 2 | 1
Abdominal Pain Upper | 2 | 2 | 3 | 3 | 2
Gastritis | 1 | 2 | 1 | 2 | 1
Transaminase increased | 1 | 5 | 2 | 2 | 1

Other infrequent and medically relevant adverse reactions occurring at an incidence less than 2% in rheumatoid arthritis patients treated with tocilizumab-IV in controlled trials were:

Infections and Infestations:oral herpes simplex
Gastrointestinal disorders:stomatitis, gastric ulcer
Investigations:weight increased, total bilirubin increased
Blood and lymphatic system disorders:leukopenia
General disorders and administration site conditions:edema peripheral
Respiratory, thoracic, and mediastinal disorders:dyspnea, cough
Eye disorders:conjunctivitis
Renal disorders:nephrolithiasis
Endocrine disorders:hypothyroidism

6.2 Clinical Trials Experience in Giant Cell Arteritis Patients Treated with Intravenous Tocilizumab (Tocilizumab-IV)

The safety of tocilizumab-IV was studied in an open label PK-PD and safety study in 24 patients with GCA who were in remission on tocilizumab-IV at time of enrollment. Patients received tocilizumab 7 mg/kg every 4 weeks for 20 weeks, followed by 6 mg/kg every 4 weeks for 20 weeks. The total patient years exposure to treatment was 17.5 years.

The safety of tocilizumab by another route of administration has been studied in one Phase III study with 251 GCA patients. The total patient years duration was 138.5 patient years during the 12-month double blind, placebo-controlled phase of the study. The overall safety profile observed was generally consistent with the known safety profile of tocilizumab. There was an overall higher incidence of infections in GCA patients relative to RA patients.

The overall safety profile observed for tocilizumab administered intravenously in GCA patients was consistent with the known safety profile of tocilizumab.

6.3 Clinical Trials Experience in Polyarticular Juvenile Idiopathic Arthritis Patients Treated with Intravenous Tocilizumab (Tocilizumab-IV)

The safety of tocilizumab-IV was studied in 188 pediatric patients 2 to 17 years of age with PJIA who had an inadequate clinical response or were intolerant to methotrexate. The total patient exposure in the tocilizumab-IV all exposure population (defined as patients who received at least one dose of tocilizumab-IV) was 184.4 patient years. At baseline, approximately half of the patients were taking oral corticosteroids and almost 80% were taking methotrexate. In general, the types of adverse drug reactions in patients with PJIA were consistent with those seen in RA and SJIA patients [see Adverse Reactions (6.1and 6.4)].

Infections

The rate of infections in the tocilizumab-IV all exposure population was 163.7 per 100 patient years. The most common events observed were nasopharyngitis and upper respiratory tract infections. The rate of serious infections was numerically higher in patients weighing less than 30 kg treated with 10 mg/kg tocilizumab (12.2 per 100 patient years) compared to patients weighing at or above 30 kg, treated with 8 mg/kg tocilizumab (4.0 per 100 patient years). The incidence of infections leading to dose interruptions was also numerically higher in patients weighing less than 30 kg treated with 10 mg/kg tocilizumab (21%) compared to patients weighing at or above 30 kg, treated with 8 mg/kg tocilizumab (8%).

Infusion Reactions

In PJIA patients, infusion-related reactions are defined as all events occurring during or within 24 hours of an infusion. In the tocilizumab-IV all exposure population, 11 patients (6%) experienced an event during the infusion, and 38 patients (20.2%) experienced an event within 24 hours of an infusion. The most common events occurring during infusion were headache, nausea and hypotension, and occurring within 24 hours of infusion were dizziness and hypotension. In general, the adverse drug reactions observed during or within 24 hours of an infusion were similar in nature to those seen in RA and SJIA patients [see Adverse Reactions (6.1and 6.4)].

No clinically significant hypersensitivity reactions associated with tocilizumab and requiring treatment discontinuation were reported.

Immunogenicity

One patient, in the 10 mg/kg less than 30 kg group, developed positive anti-tocilizumab antibodies without developing a hypersensitivity reaction and subsequently withdrew from the study.

Laboratory Abnormalities

Neutropenia

During routine laboratory monitoring in the tocilizumab-IV all exposure population, a decrease in neutrophil counts below 1 × 10^9per L occurred in 3.7% of patients.

There was no clear relationship between decreases in neutrophils below 1 × 10^9per L and the occurrence of serious infections.

Thrombocytopenia

During routine laboratory monitoring in the tocilizumab-IV all exposure population, 1% of patients had a decrease in platelet count at or less than 50,000 per mm^3without associated bleeding events.

Elevated Liver Enzymes

During routine laboratory monitoring in the tocilizumab-IV all exposure population, elevation in ALT or AST at or greater than 3 × ULN occurred in 4% and less than 1% of patients, respectively.

Lipids

During routine laboratory monitoring in the tocilizumab all exposure population, elevation in total cholesterol greater than 1.5-2 × ULN occurred in one patient (0.5%) and elevation in LDL greater than 1.5-2 × ULN occurred in one patient (0.5%).

6.4 Clinical Trials Experience in Systemic Juvenile Idiopathic Arthritis Patients Treated with Intravenous Tocilizumab (Tocilizumab-IV)

The data described below reflect exposure to tocilizumab-IV in one randomized, double-blind, placebo-controlled trial of 112 pediatric patients with SJIA 2 to 17 years of age who had an inadequate clinical response to nonsteroidal anti-inflammatory drugs (NSAIDs) or corticosteroids due to toxicity or lack of efficacy. At baseline, approximately half of the patients were taking 0.3 mg/kg/day corticosteroids or more, and almost 70% were taking methotrexate. The trial included a 12 week controlled phase followed by an open-label extension. In the 12 week double-blind, controlled portion of the clinical study 75 patients received treatment with tocilizumab-IV (8 or 12 mg per kg based upon body weight). After 12 weeks or at the time of escape, due to disease worsening, patients were treated with tocilizumab-IV in the open-label extension phase.

The most common adverse events (at least 5%) seen in tocilizumab-IV treated patients in the 12 week controlled portion of the study were: upper respiratory tract infection, headache, nasopharyngitis and diarrhea.

Infections

In the 12 week controlled phase, the rate of all infections in the tocilizumab-IV group was 345 per 100 patient-years and 287 per 100 patient-years in the placebo group. In the open label extension over an average duration of 73 weeks of treatment, the overall rate of infections was 304 per 100 patient-years.

In the 12 week controlled phase, the rate of serious infections in the tocilizumab-IV group was 11.5 per 100 patient years. In the open label extension over an average duration of 73 weeks of treatment, the overall rate of serious infections was 11.4 per 100 patient years. The most commonly reported serious infections included pneumonia, gastroenteritis, varicella, and otitis media.

Macrophage Activation Syndrome

In the 12 week controlled study, no patient in any treatment group experienced macrophage activation syndrome (MAS) while on assigned treatment; 3 per 112 (3%) developed MAS during open-label treatment with tocilizumab-IV. One patient in the placebo group escaped to tocilizumab-IV 12 mg per kg at Week 2 due to severe disease activity, and ultimately developed MAS at Day 70. Two additional patients developed MAS during the long-term extension. All 3 patients had tocilizumab-IV dose interrupted (2 patients) or discontinued (1 patient) for the MAS event, received treatment, and the MAS resolved without sequelae. Based on a limited number of cases, the incidence of MAS does not appear to be elevated in the tocilizumab-IV SJIA clinical development experience; however no definitive conclusions can be made.

Infusion Reactions

Patients were not premedicated, however most patients were on concomitant corticosteroids as part of their background treatment for SJIA. Infusion related reactions were defined as all events occurring during or within 24 hours after an infusion. In the 12 week controlled phase, 4% of tocilizumab-IV and 0% of placebo treated patients experienced events occurring during infusion. One event (angioedema) was considered serious and life-threatening, and the patient was discontinued from study treatment.

Within 24 hours after infusion, 16% of patients in the tocilizumab-IV treatment group and 5% of patients in the placebo group experienced an event. In the tocilizumab-IV group the events included rash, urticaria, diarrhea, epigastric discomfort, arthralgia and headache. One of these events, urticaria, was considered serious.

Anaphylaxis

Anaphylaxis was reported in 1 out of 112 patients (less than 1%) treated with tocilizumab-IV during the controlled and open label extension study [see Warnings and Precautions (5.6)].

Immunogenicity

All 112 patients were tested for anti-tocilizumab antibodies at baseline. Two patients developed positive anti-tocilizumab antibodies: one of these patients experienced serious adverse events of urticaria and angioedema consistent with an anaphylactic reaction which led to withdrawal; the other patient developed macrophage activation syndrome while on escape therapy and was discontinued from the study.

Laboratory Abnormalities

Neutropenia

During routine monitoring in the 12 week controlled phase, a decrease in neutrophil below 1 × 10^9per L occurred in 7% of patients in the tocilizumab-IV group, and in no patients in the placebo group. In the open label extension over an average duration of 73 weeks of treatment, a decreased neutrophil count occurred in 17% of the tocilizumab-IV group. There was no clear relationship between decrease in neutrophils below 1 × 10^9per L and the occurrence of serious infections.

Thrombocytopenia

During routine monitoring in the 12 week controlled phase, 1% of patients in the tocilizumab-IV group and 3% in the placebo group had a decrease in platelet count to no more than 100,000 per mm^3.

In the open label extension over an average duration of 73 weeks of treatment, decreased platelet count occurred in 4% of patients in the tocilizumab-IV group, with no associated bleeding.

Elevated Liver Enzymes

During routine laboratory monitoring in the 12 week controlled phase, elevation in ALT or AST at or above 3× ULN occurred in 5% and 3% of patients, respectively in the tocilizumab-IV group and in 0% of placebo patients.

In the open label extension over an average duration of 73 weeks of treatment, the elevation in ALT or AST at or above 3× ULN occurred in 13% and 5% of tocilizumab-IV treated patients, respectively.

Lipids

During routine laboratory monitoring in the 12 week controlled phase, elevation in total cholesterol greater than 1.5× ULN – 2× ULN occurred in 1.5% of the tocilizumab-IV group and in 0% of placebo patients. Elevation in LDL greater than 1.5× ULN – 2× ULN occurred in 1.9% of patients in the tocilizumab-IV group and 0% of the placebo group.

In the open label extension study over an average duration of 73 weeks of treatment, the pattern and incidence of elevations in lipid parameters remained consistent with the 12 week controlled study data.

6.5 Clinical Trials Experience in COVID-19 Patients Treated with Intravenous Tocilizumab (Tocilizumab-IV)

The safety of tocilizumab in hospitalized COVID-19 patients was evaluated in a pooled safety population that includes patients enrolled in EMPACTA, COVACTA, AND REMDACTA. The analysis of adverse reactions included a total of 974 patients exposed to tocilizumab. Patients received a single, 60-minute infusion of intravenous tocilizumab 8 mg/kg (maximum dose of 800 mg). If clinical signs or symptoms worsened or did not improve, one additional dose of tocilizumab 8 mg/kg could be administered between 8- 24 hours after the initial dose.

Adverse reactions summarized in Table 3 occurred in at least 3% of tocilizumab -treated patients and more commonly than in patients on placebo in the pooled safety population.

Table 3 Adverse Reactions [Patients are counted once for each category regardless of the number of reactions] Identified From the Pooled COVID-19 Safety Population
Adverse Reaction | Tocilizumab 8mg per kg | Placebo
 | N = 974 (%) | N = 483 (%)
Hepatic Transaminases increased | 10% | 8%
Constipation | 9% | 8%
Urinary tract infection | 5% | 4%
Hypertension | 4% | 1%
Hypokalaemia | 4% | 3%
Anxiety | 4% | 2%
Diarrhea | 4% | 2%
Insomnia | 4% | 3%
Nausea | 3% | 2%

In the pooled safety population, the rates of infection/serious infection events were 30%/19% in patients receiving tocilizumab versus 32%/23% receiving placebo.

Laboratory Abnormalities

In the pooled safety population of EMPACTA, COVACTA, and REMDACTA, neutrophil counts <1000 cells/mcl occurred in 3.4% of patients who received tocilizumab and 0.5% of patients who received placebo. Platelet counts <50,000 cells/mcl occurred in 3.2% of patients who received tocilizumab and 1.5% of patients who received placebo. ALT or AST at or above 5× ULN occurred in 11.7% of patients who received tocilizumab and 9.9% of patients who received placebo.

6.6 Postmarketing Experience

The following adverse reactions have been identified during post-approval use of tocilizumab products. Because these reactions are reported voluntarily from a population of uncertain size, it is not always possible to reliably estimate their frequency or establish a causal relationship to drug exposure.

- Hypersensitivity Reactions: Fatal anaphylaxis, Stevens-Johnson Syndrome, Drug Reaction with Eosinophilia and Systemic Symptoms (DRESS) [see Warnings and Precautions (5.6)]
- Pancreatitis
- Drug-induced liver injury, Hepatitis, Hepatic failure, Jaundice [see Warnings and Precautions (5.3)]

7 DRUG INTERACTIONS

7.1 Concomitant Drugs for Treatment of Adult Indications

In RA patients, population pharmacokinetic analyses did not detect any effect of methotrexate (MTX), non-steroidal anti-inflammatory drugs or corticosteroids on tocilizumab clearance. Concomitant administration of a single intravenous dose of 10 mg/kg tocilizumab with 10-25 mg MTX once weekly had no clinically significant effect on MTX exposure. Tocilizumab products have not been studied in combination with biological DMARDs such as TNF antagonists [see Dosage and Administration (2.2)].

In GCA patients, no effect of concomitant corticosteroid on tocilizumab exposure was observed.

7.2 Interactions with CYP450 Substrates

Cytochrome P450s in the liver are down-regulated by infection and inflammation stimuli including cytokines such as IL-6. Inhibition of IL-6 signaling in RA patients treated with tocilizumab products may restore CYP450 activities to higher levels than those in the absence of tocilizumab products leading to increased metabolism of drugs that are CYP450 substrates. In vitro studies showed that tocilizumab has the potential to affect expression of multiple CYP enzymes including CYP1A2, CYP2B6, CYP2C9, CYP2C19, CYP2D6 and CYP3A4. Its effect on CYP2C8 or transporters is unknown. In vivo studies with omeprazole, metabolized by CYP2C19 and CYP3A4, and simvastatin, metabolized by CYP3A4, showed up to a 28% and 57% decrease in exposure one week following a single dose of tocilizumab, respectively. The effect of tocilizumab products on CYP enzymes may be clinically relevant for CYP450 substrates with narrow therapeutic index, where the dose is individually adjusted. Upon initiation or discontinuation of TOFIDENCE, in patients being treated with these types of medicinal products, perform therapeutic monitoring of effect (e.g., warfarin) or drug concentration (e.g., cyclosporine or theophylline) and the individual dose of the medicinal product adjusted as needed. Exercise caution when coadministering TOFIDENCE with CYP3A4 substrate drugs where decrease in effectiveness is undesirable, e.g., oral contraceptives, lovastatin, atorvastatin, etc. The effect of tocilizumab products on CYP450 enzyme activity may persist for several weeks after stopping therapy [see Clinical Pharmacology (12.3)].

7.3 Live Vaccines

Avoid use of live vaccines concurrently with TOFIDENCE [see Warnings and Precautions (5.9)].

8 USE IN SPECIFIC POPULATIONS

8.1 Pregnancy

Risk Summary

The available data with tocilizumab products from a pregnancy exposure registry, retrospective cohort study, pharmacovigilance, and published literature are insufficient to draw conclusion about a drug-associated risk of major birth defects, miscarriage, or other adverse maternal or fetal outcomes. These studies had methodological limitations, including small sample size of tocilizumab exposed groups, missing exposure and outcomes information, and lack of adjustment for cofounders. Monoclonal antibodies, such as tocilizumab products, are actively transported across the placenta during the third trimester of pregnancy and may affect immune response in the in uteroexposed infant [see Clinical Considerations]. In animal reproduction studies, intravenous administration of tocilizumab to Cynomolgus monkeys during organogenesis caused abortion/embryo-fetal death at doses 1.25 times and higher than the maximum recommended human dose by the intravenous route of 8 mg per kg every 2 to 4 weeks. The literature in animals suggests that inhibition of IL-6 signaling may interfere with cervical ripening and dilatation and myometrial contractile activity leading to potential delays of parturition [see Data]. Based on the animal data, there may be a potential risk to the fetus.

The estimated background risk of major birth defects and miscarriage for the indicated population is unknown. All pregnancies have a background risk of birth defect, loss or other adverse outcomes. In the U.S. general population, the estimated background risk of major birth defects and miscarriage in clinically recognized pregnancies is 2 to 4% and 15 to 20%, respectively.

Clinical Considerations

Fetal/Neonatal adverse reactions

Monoclonal antibodies are increasingly transported across the placenta as pregnancy progresses, with the largest amount transferred during the third trimester. Risks and benefits should be considered prior to administering live or live-attenuated vaccines to infants exposed to TOFIDENCE in utero [see Warnings and Precautions (5.9)].

Disease-associated Maternal Risk

Published data suggest that the risk of adverse pregnancy outcomes in women with rheumatoid arthritis is associated with increased disease activity. Adverse pregnancy outcomes include preterm delivery (before 37 weeks of gestation), low birth weight (less than 2500 g) infants, and small for gestational age at birth.

Data

Animal Data

An embryo-fetal developmental toxicity study was performed in which pregnant Cynomolgus monkeys were treated intravenously with tocilizumab at daily doses of 2, 10, or 50 mg/ kg during organogenesis from gestation day (GD) 20-50. Although there was no evidence for a teratogenic/dysmorphogenic effect at any dose, tocilizumab produced an increase in the incidence of abortion/embryo-fetal death at doses 1.25 times and higher the MRHD by the intravenous route at maternal intravenous doses of 10 and 50 mg/ kg. Testing of a murine analogue of tocilizumab in mice did not yield any evidence of harm to offspring during the pre- and postnatal development phase when dosed at 50 mg/kg intravenously with treatment every three days from implantation (GD 6) until post-partum day 21 (weaning). There was no evidence for any functional impairment of the development and behavior, learning ability, immune competence and fertility of the offspring.

Parturition is associated with significant increases of IL-6 in the cervix and myometrium. The literature suggests that inhibition of IL-6 signaling may interfere with cervical ripening and dilatation and myometrial contractile activity leading to potential delays of parturition. For mice deficient in IL-6 (ll6-/-null mice), parturition was delayed relative to wild-type (ll6+/+) mice. Administration of recombinant IL-6 to ll6-/-null mice restored the normal timing of delivery.

8.2 Lactation

Risk Summary

No information is available on the presence of tocilizumab products in human milk, the effects of the drug on the breastfed infant, or the effects of the drug on milk production. Maternal immunoglobulin G (IgG) is present in human milk. If tocilizumab products are transferred into human milk, the effects of local exposure in the gastrointestinal tract and potential limited systemic exposure in the infant to tocilizumab products are unknown.

The lack of clinical data during lactation precludes clear determination of the risk of tocilizumab products to an infant during lactation; therefore the developmental and health benefits of breastfeeding should be considered along with the mother's clinical need for TOFIDENCE and the potential adverse effects on the breastfed child from Tofidence or from the underlying maternal condition.

8.4 Pediatric Use

TOFIDENCE by intravenous use is indicated for the treatment of pediatric patients with:

- Active systemic juvenile idiopathic arthritis in patients 2 years of age and older
- Active polyarticular juvenile idiopathic arthritis in patients 2 years of age and older

The safety and effectiveness of TOFIDENCE in pediatric patients with conditions other than PJIA or SJIA have not been established. The safety and effectiveness in pediatric patients below the age of 2 have not been established in PJIA or SJIA.

Systemic Juvenile Idiopathic Arthritis – Intravenous Use

A multicenter, open-label, single arm study to evaluate the PK, safety and exploratory PD and efficacy of tocilizumab over 12-weeks in SJIA patients (N=11) under 2 years of age was conducted. Patients received intravenous tocilizumab 12 mg/kg every two weeks. Concurrent use of stable background treatment with corticosteroids, MTX, and/or non-steroidal anti-inflammatory drugs was permitted. Patients who completed the 12-week period could continue to the optional extension period (a total of 52-weeks or until the age of 2 years, whichever was longer).

The primary PK endpoints (Cmax, Ctroughand AUC2weeks) of tocilizumab at steady-state in this study were within the ranges of these parameters observed in patients with SJIA aged 2 to 17 years.

The safety and immunogenicity of tocilizumab for patients with SJIA under 2 years of age was assessed descriptively. SAEs, AEs leading to discontinuation, and infectious AEs were reported by 27.3%, 36.4%, and 81.8% of patients. Six patients (54.5%) experienced hypersensitivity reactions, defined as all adverse events occurring during or within 24 hours after an infusion considered related to tocilizumab. Three of these patients experienced serious hypersensitivity reactions and were withdrawn from the study. Three patients with hypersensitivity reactions (two with serious hypersensitivity reactions) developed treatment induced anti-tocilizumab antibodies after the event. There were no cases of MAS based on the protocol-specified criteria, but 2 cases of suspected MAS based on Ravelli criteria [Ravelli A, Minoia F, Davì S on behalf of the Paediatric Rheumatology International Trials Organisation, the Childhood Arthritis and Rheumatology Research Alliance, the Pediatric Rheumatology Collaborative Study Group, and the Histiocyte Society, et al. 2016 Classification Criteria for Macrophage Activation Syndrome Complicating Systemic Juvenile Idiopathic Arthritis. Annals of the Rheumatic Diseases 2016;75:481-489.] .

8.5 Geriatric Use

Of the 2644 patients who received tocilizumab in Studies I to V [see Clinical Studies (14)], a total of 435 rheumatoid arthritis patients were 65 years of age and older, including 50 patients 75 years and older. The frequency of serious infection among tocilizumab treated subjects 65 years of age and older was higher than those under the age of 65. As there is a higher incidence of infections in the elderly population in general, caution should be used when treating the elderly.

In the EMPACTA, COVACTA, and REMDACTA studies, of the 974 COVID-19 patients in the tocilizumab arm, 375 (39%) were 65 years of age or older. No overall differences in safety or effectiveness of tocilizumab were observed between patients 65 years of age and older and those under the age of 65 years of age in these studies [see Adverse Reactions (6.5)and Clinical Studies (14.5)] .

In the RECOVERY study, of the 2022 COVID-19 patients in the tocilizumab arm, 930 (46%) were 65 years of age or older. No overall differences in effectiveness of tocilizumab were observed between patients 65 years of age and older and those under the age 65 years of age in this study [see Clinical Studies (14.5)] .

8.6 Hepatic Impairment

The safety and efficacy of tocilizumab products have not been studied in patients with hepatic impairment, including patients with positive HBV and HCV serology [see Warnings and Precautions (5.8)].

8.7 Renal Impairment

No dose adjustment is required in patients with mild or moderate renal impairment. Tocilizumab products have not been studied in patients with severe renal impairment [see Clinical Pharmacology (12.3)].

9 DRUG ABUSE AND DEPENDENCE

No studies on the potential for tocilizumab products to cause dependence have been performed. However, there is no evidence from the available data that tocilizumab products treatment results in dependence.

10 OVERDOSAGE

There are limited data available on overdoses with tocilizumab products. One case of accidental overdose was reported with intravenous tocilizumab in which a patient with multiple myeloma received a dose of 40 mg per kg. No adverse drug reactions were observed. No serious adverse drug reactions were observed in healthy volunteers who received single doses of up to 28 mg per kg, although all 5 patients at the highest dose of 28 mg per kg developed dose-limiting neutropenia.

In case of an overdose, it is recommended that the patient be monitored for signs and symptoms of adverse reactions. Patients who develop adverse reactions should receive appropriate symptomatic treatment.

11 DESCRIPTION

Tocilizumab-bavi is a recombinant humanized anti-human interleukin 6 (IL-6) receptor monoclonal antibody of the immunoglobulin IgG1κ (gamma 1, kappa) subclass with a typical H2L2polypeptide structure. Each light chain and heavy chain consists of 214 and 448 amino acids, respectively. The four polypeptide chains are linked intra- and inter-molecularly by disulfide bonds. Tocilizumab-bavi has a molecular weight of approximately 148 kDa. The antibody is produced in mammalian (Chinese hamster ovary) cells.

Intravenous Infusion

TOFIDENCE (tocilizumab-bavi) injection is a sterile, clear to opalescent, colorless to light yellow, preservative-free solution for further dilution prior to intravenous infusion with a pH of approximately 6.2. Each single-dose vial, formulated in an aqueous solution, is available at a concentration of 20 mg/mL containing 80 mg/4 mL, 200 mg/10 mL, or 400 mg/20 mL of TOFIDENCE. Each mL of solution contains arginine hydrochloride (10.53 mg), histidine (0.81 mg), L-histidine hydrochloride monohydrate (1.01 mg), polysorbate 80 (0.5 mg), sucrose (20 mg), and water for injection.

12 CLINICAL PHARMACOLOGY

12.1 Mechanism of Action

Tocilizumab products bind to both soluble and membrane-bound IL-6 receptors (sIL-6R and mIL-6R), and have been shown to inhibit IL-6-mediated signaling through these receptors. IL-6 is a pleiotropic pro-inflammatory cytokine produced by a variety of cell types including T- and B-cells, lymphocytes, monocytes and fibroblasts. IL-6 has been shown to be involved in diverse physiological processes such as T-cell activation, induction of immunoglobulin secretion, initiation of hepatic acute phase protein synthesis, and stimulation of hematopoietic precursor cell proliferation and differentiation. IL-6 is also produced by synovial and endothelial cells leading to local production of IL-6 in joints affected by inflammatory processes such as rheumatoid arthritis.

12.2 Pharmacodynamics

In clinical studies in RA patients with the 4 mg per kg and 8 mg per kg intravenous doses decreases in levels of C-reactive protein (CRP) to within normal ranges were seen as early as week 2. Changes in pharmacodynamic parameters were observed (i.e., decreases in rheumatoid factor, erythrocyte sedimentation rate (ESR), serum amyloid A, fibrinogen and increases in hemoglobin) with doses, however the greatest improvements were observed with 8 mg per kg tocilizumab. Pharmacodynamic changes were also observed to occur after tocilizumab administration in GCA, PJIA, and SJIA patients (decreases in CRP, ESR, and increases in hemoglobin). The relationship between these pharmacodynamic findings and clinical efficacy is not known.

In healthy subjects administered tocilizumab in doses from 2 to 28 mg per kg intravenously, absolute neutrophil counts decreased to the nadir 3 to 5 days following tocilizumab administration. Thereafter, neutrophils recovered towards baseline in a dose dependent manner. Rheumatoid arthritis and GCA patients demonstrated a similar pattern of absolute neutrophil counts following tocilizumab administration [see Warnings and Precautions (5.4)].

12.3 Pharmacokinetics

PK of tocilizumab is characterized by nonlinear elimination which is a combination of linear clearance and Michaelis-Menten elimination. The nonlinear part of tocilizumab elimination leads to an increase in exposure that is more than dose-proportional. The pharmacokinetic parameters of tocilizumab do not change with time. Due to the dependence of total clearance on tocilizumab serum concentrations, the half-life of tocilizumab is also concentration-dependent and varies depending on the serum concentration level. Population pharmacokinetic analyses in any patient population tested so far indicate no relationship between apparent clearance and the presence of anti-drug antibodies.

Rheumatoid Arthritis - Intravenous Administration

The pharmacokinetics in healthy subjects and RA patients suggest that PK is similar between the two populations.

The population PK model was developed from an analysis dataset composed of an IV dataset of 1793 patients from Study I, Study III, Study IV, and Study V. Cmeanis included in place of AUCtau, since for dosing regimens with different inter-dose intervals, the mean concentration over the dosing period characterizes the comparative exposure better than AUCtau.

At high serum concentrations, when total clearance of tocilizumab is dominated by linear clearance, a terminal half-life of approximately 21.5 days was derived from the population parameter estimates.

For doses of 4 mg/kg tocilizumab given every 4 weeks intravenously, the estimated median (range) Cmax, Ctrough, and Cmeanof tocilizumab at steady state were 86.1 (44.8–202) mcg/mL, 0.1 (0.0–14.6) mcg/mL, and 18.0 (8.9–50.7) mcg/mL, respectively. For doses of 8 mg/kg tocilizumab given every 4 weeks intravenously, the estimated median (range) Cmax, Ctrough, and Cmeanof tocilizumab were 176 (75.4–557) mcg/mL, 13.4 (0.1–154) mcg/mL, and 54.0 (17–260) mcg/mL, respectively. Cmaxincreased dose-proportionally between doses of 4 and 8 mg/kg IV every 4 weeks, while a greater than dose-proportional increase was observed in Cmeanand Ctrough. At steady-state, Cmeanand Ctroughwere 3.0 and 134 fold higher at 8 mg/kg as compared to 4 mg/kg, respectively.

The accumulation ratios for AUC and Cmaxafter multiple doses of 4 and 8 mg/kg IV Q4W are low, while the accumulation ratios for Ctroughare higher (2.62 and 2.47, respectively). For Cmax, greater than 90% of the steady-state value was reached after the 1st IV infusion. For AUCtauand Cmean, 90% of the steady-state value was reached after the 1st and 3rd infusion for 4 mg/kg and 8 mg/kg IV, while for Ctrough, approximately 90% of the steady-state value was reached after the 4th IV infusion after both doses.

Population PK analysis identified body weight as a significant covariate impacting the pharmacokinetics of tocilizumab. When given IV on a mg/kg basis, individuals with body weight ≥ 100 kg are predicted to have mean steady-state exposures higher than mean values for the patient population. Therefore, tocilizumab doses exceeding 800 mg per infusion are not recommended in patients with RA [see Dosage and Administration (2.1)].

Giant Cell Arteritis – Intravenous Administration

The pharmacokinetics of tocilizumab IV in GCA patients was characterized by a non-compartmental pharmacokinetic analysis which included 22 patients treated with 6 mg/kg intravenously every 4 weeks for 20 weeks. The median (range) Cmax, Ctroughand Cmeanof tocilizumab at steady state were 178 (115-320) mcg/mL, 22.7 (3.38-54.5) mcg/mL and 57.5 (32.9-110) mcg/mL, respectively. Steady state trough concentrations were within the range observed in GCA patients treated with tocilizumab by another route of administration.

Based on pharmacokinetic exposure and extrapolation between RA and GCA patients, when given IV on a mg/kg basis, tocilizumab doses exceeding 600 mg per infusion are not recommended in patients with GCA [see Dosage and Administration (2.3)].

Polyarticular Juvenile Idiopathic Arthritis – Intravenous Administration

The pharmacokinetics of tocilizumab (TCZ) in PJIA patients was characterized by a population pharmacokinetic analysis which included 188 patients who were treated with TCZ IV.

For doses of 8 mg/kg tocilizumab (patients with a body weight at or above 30 kg) given every 4 weeks intravenously, the estimated median (range) Cmax, Ctrough, and Cmeanof tocilizumab at steady state were 181 (114–331) mcg/mL, 3.28 (0.02–35.4) mcg/mL, and 38.6 (22.2–83.8) mcg/mL, respectively. For doses of 10 mg/kg tocilizumab (patients with a body weight less than 30 kg) given every 4 weeks intravenously, the estimated median (range) Cmax, Ctrough, and Cmeanof tocilizumab were 167 (125–220) mcg/mL, 0.35 (0–11.8) mcg/mL, and 30.8 (16.0–48.0) mcg/mL, respectively.

The accumulation ratios were 1.05 and 1.16 for AUC4weeks, and 1.43 and 2.22 for Ctroughfor 10 mg/kg (BW less than 30 kg) and 8 mg/kg (BW at or above 30 kg) intravenous doses, respectively. No accumulation for Cmaxwas observed. Following 10 mg/kg and 8 mg/kg TCZ IV every 4 weeks doses in PJIA patients (aged 2 to 17 years), steady state concentrations (trough and average) were within the range of exposures in adult RA patients following 4 mg/kg and 8 mg/kg every 4 weeks, and steady state peak concentrations in PJIA patients were comparable to those following 8 mg/kg every 4 weeks in adult RA patients.

Systemic Juvenile Idiopathic Arthritis—Intravenous Administration

The pharmacokinetics of tocilizumab (TCZ) in SJIA patients was characterized by a population pharmacokinetic analysis which included 89 patients who were treated with TCZ IV.

For doses of 8 mg/kg tocilizumab (patients with a body weight at or above 30 kg) given every 2 weeks intravenously, the estimated median (range) Cmax, Ctrough, and Cmeanof tocilizumab were 253 (120–404) mcg/mL, 70.7 (5.26–127) mcg/mL, and 117 (37.6–199) mcg/mL, respectively. For doses of 12 mg/kg tocilizumab (patients with a body weight less than 30 kg) given every 2 weeks intravenously, the estimated median (range) Cmax, Ctrough, and Cmeanof tocilizumab were 274 (149–444) mcg/mL, 65.9 (19.0–135) mcg/mL, and 124 (60–194) mcg/mL, respectively.

The accumulation ratios were 1.95 and 2.01 for AUC4weeks, and 3.41 and 3.20 for Ctroughfor 12 mg/kg (BW less than 30 kg) and 8 mg/kg (BW at or above 30 kg) intravenous doses, respectively. Accumulation data for Cmaxwere 1.37 and 1.42 for 12 mg/kg (BW less than 30 kg) and 8 mg/kg (BW at or above 30 kg) intravenous doses, respectively. Following every other week dosing with tocilizumab IV, steady state was reached by 8 weeks for both body weight groups. Mean estimated tocilizumab exposure parameters were similar between the two dose groups defined by body weight.

COVID-19 -Intravenous Administration

The pharmacokinetics of tocilizumab in COVID-19 patients was characterized by a population pharmacokinetic analysis of a dataset composed of 380 adult patients treated with tocilizumab 8mg/kg intravenously (IV) in the COVACTA study [see Clinical Studies (14.5)] and another clinical study.

For one dose of 8 mg/kg tocilizumab IV, the estimated median (range) Cmaxand Cday28of tocilizumab were 151 (77.5-319) mcg/mL and 0.229 (0.00119-19.4) mcg/mL, respectively. For two doses of 8 mg/kg tocilizumab IV separated by at least 8 hours, the estimated median (range) Cmax and Cday28 of tocilizumab was 290 (152-604) mcg/mL and 7.04 (0.00474-54.8) mcg/mL, respectively. The weight-tiered dosing used in RECOVERY study, 800 mg for patients >90 kg, 600 mg for patients >65 and ≤90 kg, 400 mg for patients >40 and ≤65 kg, and 8mg/kg for patients ≤40 kg, is comparable to 8 mg/kg dosing and is expected to have similar exposure.

Distribution

Following intravenous dosing, tocilizumab undergoes biphasic elimination from the circulation. In rheumatoid arthritis patients the central volume of distribution was 3.5 L and the peripheral volume of distribution was 2.9 L, resulting in a volume of distribution at steady state of 6.4 L.

In GCA patients, the central volume of distribution was 4.09 L, the peripheral volume of distribution was 3.37 L resulting in a volume of distribution at steady state of 7.46 L.

In pediatric patients with PJIA, the central volume of distribution was 1.98 L, the peripheral volume of distribution was 2.1 L, resulting in a volume of distribution at steady state of 4.08 L.

In pediatric patients with SJIA, the central volume of distribution was 1.87 L, the peripheral volume of distribution was 2.14 L resulting in a volume of distribution at steady state of 4.01 L.

In COVID-19 patients treated with one or two infusions of tocilizumab 8 mg/kg intravenously separated by 8 hours, the estimated central volume of distribution was 4.52 L, and the estimated peripheral volume of distribution was 4.23 L, resulting in a volume of distribution of 8.75 L.

Elimination

Tocilizumab is eliminated by a combination of linear clearance and nonlinear elimination. The concentration-dependent nonlinear elimination plays a major role at low tocilizumab concentrations. Once the nonlinear pathway is saturated, at higher tocilizumab concentrations, clearance is mainly determined by the linear clearance. The saturation of the nonlinear elimination leads to an increase in exposure that is more than dose-proportional. The pharmacokinetic parameters of tocilizumab do not change with time.

Population pharmacokinetic analyses in any patient population tested so far indicate no relationship between apparent clearance and the presence of anti-drug antibodies.

The linear clearance in the population pharmacokinetic analysis was estimated to be 12.5 mL per h in RA patients, 6.7 mL per h in GCA patients, 5.8 mL per h in pediatric patients with PJIA, and 5.7 mL per h in pediatric patients with SJIA. In COVID-19 patients, serum concentrations were below the limit of quantification after 35 days on average following one infusion of tocilizumab 8 mg/kg intravenously. The average linear clearance in the population pharmacokinetic analysis was estimated to be 17.6 mL per hour in patients with baseline ordinal scale category 3 (OS 3, patients requiring supplemental oxygen), 22.5 mL per hour in patients with baseline OS 4 (patients requiring high-flow oxygen or non-invasive ventilation), 29 mL per hour in patients with baseline OS 5 (patients requiring mechanical ventilation), and 35.4 mL per hour in patients with baseline OS 6 (patients requiring extracorporeal membrane oxygenation (ECMO) or mechanical ventilation and additional organ support).

Due to the dependence of total clearance on tocilizumab serum concentrations, the half-life of tocilizumab is also concentration-dependent and varies depending on the serum concentration level.

For intravenous administration in RA patients, the concentration-dependent apparent t1/2is up to 11 days for 4 mg per kg and up to 13 days for 8 mg per kg every 4 weeks in patients with RA at steady-state.

For intravenous administration in GCA patients, the TCZ concentration-dependent apparent t1/2was 13.2 days following 6 mg/kg every 4 weeks.

The t1/2of tocilizumab in children with PJIA is up to 17 days for the two body weight categories (8 mg/kg for body weight at or above 30 kg or 10 mg/kg for body weight below 30 kg) during a dosing interval at steady state.

The t1/2of tocilizumab intravenous in pediatric patients with SJIA is up to 16 days for the two body weight categories (8 mg/kg for body weight at or above 30 kg and 12 mg/kg for body weight below 30 kg every other week) during a dosing interval at steady-state.

Specific Populations

Population pharmacokinetic analyses in adult rheumatoid arthritis patients and GCA patients showed that age, gender and race did not affect the pharmacokinetics of tocilizumab. Linear clearance was found to increase with body size. In RA patients, the body weight-based dose (8 mg per kg) resulted in approximately 86% higher exposure in patients who are greater than 100 kg in comparison to patients who are less than 60 kg.

In COVID-19 patients, exposure following body-weight-based intravenous dosing (8 mg per kg tocilizumab up to 100 kg body weight with a maximum dose of 800 mg) was dependent on body weight and disease severity assessed by an ordinal scale (OS). Within an OS category, compared to patients with a mean body weight of 80 kg, exposure was 20% lower in patients weighing less than 60 kg. Exposure in patients weighing more than 100 kg was in the same range as exposure in patients with a mean body weight of 80 kg. For an 80 kg patient, exposure decreases as OS category increases; for each category increase, exposure decreases by 13%.

Patients with Hepatic Impairment

No formal study of the effect of hepatic impairment on the pharmacokinetics of tocilizumab was conducted.

Patients with Renal Impairment

No formal study of the effect of renal impairment on the pharmacokinetics of tocilizumab was conducted.

Most of the RA and GCA patients in the population pharmacokinetic analysis had normal renal function or mild renal impairment. Mild renal impairment (estimated creatinine clearance less than 80 mL per min and at or above 50 mL per min based on Cockcroft-Gault formula) did not impact the pharmacokinetics of tocilizumab.

No dose adjustment is required in patients with mild or moderate renal impairment.

Drug Interaction Studies

In vitro data suggested that IL-6 reduced mRNA expression for several CYP450 isoenzymes including CYP1A2, CYP2B6, CYP2C9, CYP2C19, CYP2D6 and CYP3A4, and this reduced expression was reversed by co-incubation with tocilizumab at clinically relevant concentrations. Accordingly, inhibition of IL-6 signaling in RA patients treated with tocilizumab may restore CYP450 activities to higher levels than those in the absence of tocilizumab leading to increased metabolism of drugs that are CYP450 substrates. Its effect on CYP2C8 or transporters (e.g., P-gp) is unknown. This is clinically relevant for CYP450 substrates with a narrow therapeutic index, where the dose is individually adjusted. Upon initiation of TOFIDENCE , in patients being treated with these types of medicinal products, therapeutic monitoring of the effect (e.g., warfarin) or drug concentration (e.g., cyclosporine or theophylline) should be performed and the individual dose of the medicinal product adjusted as needed. Caution should be exercised when TOFIDENCE is coadministered with drugs where decrease in effectiveness is undesirable, e.g., oral contraceptives (CYP3A4 substrates) [see Drug Interactions (7.2)].

Simvastatin

Simvastatin is a CYP3A4 and OATP1B1 substrate. In 12 RA patients not treated with tocilizumab, receiving 40 mg simvastatin, exposures of simvastatin and its metabolite, simvastatin acid, was 4- to 10-fold and 2-fold higher, respectively, than the exposures observed in healthy subjects. One week following administration of a single infusion of tocilizumab (10 mg per kg), exposure of simvastatin and simvastatin acid decreased by 57% and 39%, respectively, to exposures that were similar or slightly higher than those observed in healthy subjects. Exposures of simvastatin and simvastatin acid increased upon withdrawal of tocilizumab in RA patients. Selection of a particular dose of simvastatin in RA patients should take into account the potentially lower exposures that may result after initiation of TOFIDENCE, (due to normalization of CYP3A4) or higher exposures after discontinuation of TOFIDENCE.

Omeprazole

Omeprazole is a CYP2C19 and CYP3A4 substrate. In RA patients receiving 10 mg omeprazole, exposure to omeprazole was approximately 2 fold higher than that observed in healthy subjects. In RA patients receiving 10 mg omeprazole, before and one week after tocilizumab infusion (8 mg per kg), the omeprazole AUCinf decreased by 12% for poor (N=5) and intermediate metabolizers (N=5) and by 28% for extensive metabolizers (N=8) and were slightly higher than those observed in healthy subjects.

Dextromethorphan

Dextromethorphan is a CYP2D6 and CYP3A4 substrate. In 13 RA patients receiving 30 mg dextromethorphan, exposure to dextromethorphan was comparable to that in healthy subjects. However, exposure to its metabolite, dextrorphan (a CYP3A4 substrate), was a fraction of that observed in healthy subjects. One week following administration of a single infusion of tocilizumab (8 mg per kg), dextromethorphan exposure was decreased by approximately 5%. However, a larger decrease (29%) in dextrorphan levels was noted after tocilizumab infusion.

13 NONCLINICAL TOXICOLOGY

13.1 Carcinogenesis, Mutagenesis, Impairment of Fertility

No long-term animal studies have been performed to establish the carcinogenicity potential of tocilizumab products. Literature indicates that the IL-6 pathway can mediate anti-tumor responses by promoting increased immune cell surveillance of the tumor microenvironment. However, available published evidence also supports that IL-6 signaling through the IL-6 receptor may be involved in pathways that lead to tumorigenesis. The malignancy risk in humans from an antibody that disrupts signaling through the IL-6 receptor, such as tocilizumab, is presently unknown.

Fertility and reproductive performance were unaffected in male and female mice that received a murine analogue of tocilizumab administered by the intravenous route at a dose of 50 mg/kg every three days.

14 CLINICAL STUDIES

14.1 Rheumatoid Arthritis—Intravenous Administration

The efficacy and safety of intravenously administered tocilizumab was assessed in five randomized, double-blind, multicenter studies in patients greater than 18 years with active rheumatoid arthritis diagnosed according to American College of Rheumatology (ACR) criteria. Patients had at least 8 tender and 6 swollen joints at baseline. Tocilizumab was given intravenously every 4 weeks as monotherapy (Study I), in combination with methotrexate (MTX) (Studies II and III) or other disease-modifying anti-rheumatic drugs (DMARDs) (Study IV) in patients with an inadequate response to those drugs, or in combination with MTX in patients with an inadequate response to TNF antagonists (Study V).

Study I(NCT00109408) evaluated patients with moderate to severe active rheumatoid arthritis who had not been treated with MTX within 24 weeks prior to randomization, or who had not discontinued previous methotrexate treatment as a result of clinically important toxic effects or lack of response. In this study, 67% of patients were MTX-naïve, and over 40% of patients had rheumatoid arthritis less than 2 years. Patients received tocilizumab 8 mg per kg monotherapy or MTX alone (dose titrated over 8 weeks from 7.5 mg to a maximum of 20 mg weekly). The primary endpoint was the proportion of tocilizumab patients who achieved an ACR 20 response at Week 24.

Study II(NCT00106535) was a 104-week study with an optional 156-week extension phase that evaluated patients with moderate to severe active rheumatoid arthritis who had an inadequate clinical response to MTX. Patients received tocilizumab 8 mg per kg, tocilizumab 4 mg per kg, or placebo every four weeks, in combination with MTX (10 to 25 mg weekly). Upon completion of 52-weeks, patients received open-label treatment with tocilizumab 8 mg per kg through 104 weeks or they had the option to continue their double-blind treatment if they maintained a greater than 70% improvement in swollen/tender joint count. Two pre-specified interim analyses at week 24 and week 52 were conducted. The primary endpoint at week 24 was the proportion of patients who achieved an ACR 20 response. At weeks 52 and 104, the primary endpoints were change from baseline in modified total Sharp-Genant score and the area under the curve (AUC) of the change from baseline in HAQ-DI score.

Study III(NCT00106548) evaluated patients with moderate to severe active rheumatoid arthritis who had an inadequate clinical response to MTX. Patients received tocilizumab 8 mg per kg, tocilizumab 4 mg per kg, or placebo every four weeks, in combination with MTX (10 to 25 mg weekly). The primary endpoint was the proportion of patients who achieved an ACR 20 response at week 24.

Study IV(NCT00106574) evaluated patients who had an inadequate response to their existing therapy, including one or more DMARDs. Patients received tocilizumab 8 mg per kg or placebo every four weeks, in combination with the stable DMARDs. The primary endpoint was the proportion of patients who achieved an ACR 20 response at week 24.

Study V(NCT00106522) evaluated patients with moderate to severe active rheumatoid arthritis who had an inadequate clinical response or were intolerant to one or more TNF antagonist therapies. The TNF antagonist therapy was discontinued prior to randomization. Patients received tocilizumab 8 mg per kg, tocilizumab 4 mg per kg, or placebo every four weeks, in combination with MTX (10 to 25 mg weekly). The primary endpoint was the proportion of patients who achieved an ACR 20 response at week 24.

Clinical Response

The percentages of intravenous tocilizumab-treated patients achieving ACR 20, 50 and 70 responses are shown in Table 4. In all intravenous studies, patients treated with 8 mg per kg tocilizumab had higher ACR 20, ACR 50, and ACR 70 response rates versus MTX- or placebo-treated patients at week 24.

During the 24 week controlled portions of Studies I to V, patients treated with tocilizumab at a dose of 4 mg per kg in patients with inadequate response to DMARDs or TNF antagonist therapy had lower response rates compared to patients treated with tocilizumab 8 mg per kg.

Table 4 Clinical Response at Weeks 24 and 52 in Active and Placebo Controlled Trials of Intravenous Tocilizumab (Percent of Patients)
Percent of Patients
Response Rate | Study I |  | Study II |  |  | Study III |  |  | Study IV |  | Study V
Response Rate | MTX | Tocilizumab 8 mg per kg | Placebo + MTX | Tocilizumab 4 mg per kg + MTX | Tocilizumab 8 mg per kg + MTX | Placebo + MTX | Tocilizumab 4 mg per kg + MTX | Tocilizumab 8 mg per kg + MTX | Placebo + DMARDs | Tocilizumab 8 mg per kg + DMARDs | Placebo + MTX | Tocilizumab 4 mg per kg + MTX | Tocilizumab 8 mg per kg + MTX
Response Rate | N=284 | N=286 | N=393 | N=399 | N=398 | N=204 | N=213 | N=205 | N=413 | N=803 | N=158 | N=161 | N=170
Response Rate |  | (95% CI) [CI: 95% confidence interval of the weighted difference to placebo adjusted for site (and disease duration for Study I only)] |  | (95% CI) | (95% CI) |  | (95% CI) | (95% CI) |  | (95% CI) | (95% CI) | (95% CI) | (95% CI)
ACR 20
Week 24 | 53% | 70% (0.11, 0.27) | 27% | 51% (0.17, 0.29) | 56% (0.23, 0.35) | 27% | 48% (0.15, 0.32) | 59% (0.23, 0.41) | 24% | 61% (0.30, 0.40) | 10% | 30% (0.15, 0.36) | 50% (0.36, 0.56)
Week 52 | N/A | N/A | 25% | 47% (0.15, 0.28) | 56% (0.25, 0.38) | N/A | N/A | N/A | N/A | N/A | N/A | N/A | N/A
ACR 50
Week 24 | 34% | 44% (0.04, 0.20) | 10% | 25% (0.09, 0.20) | 32% (0.16, 0.28) | 11% | 32% (0.13, 0.29) | 44% (0.25, 0.41) | 9% | 38% (0.23, 0.33) | 4% | 17% (0.05, 0.25) | 29% (0.21, 0.41)
Week 52 | N/A | N/A | 10% | 29% (0.14, 0.25) | 36% (0.21, 0.32) | N/A | N/A | N/A | N/A | N/A | N/A | N/A | N/A
ACR 70
Week 24 | 15% | 28% (0.07, 0.22) | 2% | 11% (0.03, 0.13) | 13% (0.05, 0.15) | 2% | 12% (0.04, 0.18) | 22% (0.12, 0.27) | 3% | 21% (0.13, 0.21) | 1% | 5% (-0.06, 0.14) | 12% (0.03, 0.22)
Week 52 | N/A | N/A | 4% | 16% (0.08, 0.17) | 20% (0.12, 0.21) | N/A | N/A | N/A | N/A | N/A | N/A | N/A | N/A
Major Clinical Responses [Major clinical response is defined as achieving an ACR 70 response for a continuous 24 week period]
Week 52 | N/A | N/A | 1% | 4% (0.01, 0.06) | 7% (0.03, 0.09) | N/A | N/A | N/A | N/A | N/A | N/A | N/A | N/A

In study II, a greater proportion of patients treated with 4 mg per kg and 8 mg per kg tocilizumab + MTX achieved a low level of disease activity as measured by a DAS 28-ESR less than 2.6 compared with placebo +MTX treated patients at week 52. The proportion of tocilizumab-treated patients achieving DAS 28-ESR less than 2.6, and the number of residual active joints in these responders in Study II are shown in Table 5.

Table 5 Proportion of Patients with DAS28-ESR Less Than 2.6 with Number of Residual Active Joints in Trials of Intravenous Tocilizumab
Study II
 | Placebo + MTX | Tocilizumab 4 mg per kg + MTX | Tocilizumab 8 mg per kg + MTX
 | N = 393 | N = 399 | N = 398
DAS28-ESR less than 2.6
Proportion of responders at week 52 (n) 95% confidence interval | 3% (12) | 18% (70) 0.10, 0.19 | 32% (127) 0.24, 0.34
Of responders, proportion with 0 active joints (n) | 33% (4) | 27% (19) | 21% (27)
Of responders, proportion with 1 active joint (n) | 8% (1) | 19% (13) | 13% (16)
Of responders, proportion with 2 active joints (n) | 25% (3) | 13% (9) | 20% (25)
Of responders, proportion with 3 or more active joints (n) | 33% (4) | 41% (29) | 47% (59)
*n denotes numerator of all the percentage. Denominator is the intent-to-treat population. Not all patients received DAS28 assessments at Week 52.

The results of the components of the ACR response criteria for Studies III and V are shown in Table 6. Similar results to Study III were observed in Studies I, II and IV.

Table 6 Components of ACR Response at Week 24 in Trials of Intravenous Tocilizumab
 | Study III |  |  |  |  |  | Study V
 | Tocilizumab 4 mg per kg + MTX |  | Tocilizumab 8 mg per kg + MTX |  | Placebo + MTX |  | Tocilizumab 4 mg per kg + MTX |  | Tocilizumab 8 mg per kg + MTX |  | Placebo + MTX
 | N=213 |  | N=205 |  | N=204 |  | N=161 |  | N=170 |  | N=158
Component (mean) | Baseline | Week 24 [Data shown is mean at week 24, difference in adjusted mean change from baseline compared with placebo + MTX at week 24 and 95% confidence interval for that difference] | Baseline | Week 24 | Baseline | Week 24 | Baseline | Week 24 | Baseline | Week 24 | Baseline | Week 24
Number of tender joints (0-68) | 33 | 19 -7.0 (-10.0, -4.1) | 32 | 14.5 -9.6 (-12.6, -6.7) | 33 | 25 | 31 | 21 -10.8 (-14.6, -7.1) | 32 | 17 -15.1 (-18.8, -11.4) | 30 | 30
Number of swollen joints (0-66) | 20 | 10 -4.2 (-6.1, -2.3) | 19.5 | 8 -6.2 (-8.1, -4.2) | 21 | 15 | 19.5 | 13 -6.2 (-9.0, -3.5) | 19 | 11 -7.2 (-9.9, -4.5) | 19 | 18
Pain [Visual analog scale: 0 = best, 100 = worst] | 61 | 33 -11.0 (-17.0, -5.0) | 60 | 30 -15.8 (-21.7, -9.9) | 57 | 43 | 63.5 | 43 -12.4 (-22.1, -2.1) | 65 | 33 -23.9 (-33.7, -14.1) | 64 | 48
Patient global assessment | 66 | 34 -10.9 (-17.1, -4.8) | 65 | 31 -14.9 (-20.9, -8.9) | 64 | 45 | 70 | 46 -10.0 (-20.3, 0.3) | 70 | 36 -17.4 (-27.8, -7.0) | 71 | 51
Physician global assessment | 64 | 26 -5.6 (-10.5, -0.8) | 64 | 23 -9.0 (-13.8, -4.2) | 64 | 32 | 66.5 | 39 -10.5 (-18.6, -2.5) | 66 | 28 -18.2 (-26.3, -10.0) | 67.5 | 43
Disability index (HAQ) [Health Assessment Questionnaire: 0 = best, 3 = worst; 20 questions; 8 categories: dressing and grooming, arising, eating, walking, hygiene, reach, grip, and activities] | 1.64 | 1.01 -0.18 (-0.34, -0.02) | 1.55 | 0.96 -0.21 (-0.37, -0.05) | 1.55 | 1.21 | 1.67 | 1.39 -0.25 (-0.42, -0.09) | 1.75 | 1.34 -0.34 (-0.51, -0.17) | 1.70 | 1.58
CRP (mg per dL) | 2.79 | 1.17 -1.30 (-2.0, -0.59) | 2.61 | 0.25 -2.156 (-2.86, -1.46) | 2.36 | 1.89 | 3.11 | 1.77 -1.34 (-2.5, -0.15) | 2.80 | 0.28 -2.52 (-3.72, -1.32) | 3.705 | 3.06

The percent of ACR 20 responders by visit for Study III is shown in Figure 1. Similar response curves were observed in studies I, II, IV, and V.

Figure 1 Percent of ACR 20 Responders by Visit for Study III (Inadequate Response to MTX) [The same patients may not have responded at each timepoint.]

Radiographic Response

In Study II, structural joint damage was assessed radiographically and expressed as change in total Sharp-Genant score and its components, the erosion score and joint space narrowing score. Radiographs of hands/wrists and forefeet were obtained at baseline, 24 weeks, 52 weeks, and 104 weeks and scored by readers unaware of treatments group and visit number. The results from baseline to week 52 are shown in Table 7. tocilizumab 4 mg per kg slowed (less than 75% inhibition compared to the control group) and tocilizumab 8 mg per kg inhibited (at least 75% inhibition compared to the control group) the progression of structural damage compared to placebo plus MTX at week 52.

Table 7 Mean Radiographic Change from Baseline to Week 52 in Study II
 | Placebo + MTX | Tocilizumab 4 mg per kg + MTX | Tocilizumab 8 mg per kg + MTX
 | N=294 | N=343 | N=353
Week 52 [Week 52 analysis employs linearly extrapolated data for patients after escape, withdrawal, or loss to follow up.]
Total Sharp-Genant Score, Mean (SD) | 1.17 (3.14) | 0.33 (1.30) | 0.25 (0.98)
Adjusted Mean difference [Difference between the adjusted means (tocilizumab + MTX - Placebo + MTX)] (95%CI) |  | -0.83 (-1.13, -0.52) | -0.90 (-1.20, -0.59)
Erosion Score, Mean (SD) | 0.76 (2.14) | 0.20 (0.83) | 0.15 (0.77)
Adjusted Mean difference (95%CI) |  | -0.55 (-0.76, -0.34) | -0.60 (-0.80, -0.39)
Joint Space Narrowing Score, Mean (SD) | 0.41 (1.71) | 0.13 (0.72) | 0.10 (0.49)
Adjusted Mean difference (95%CI) |  | -0.28 (-0.44, -0.11) | -0.30 (-0.46, -0.14)
SD = standard deviation

The mean change from baseline to week 104 in Total Sharp-Genant Score for the tocilizumab 4 mg per kg groups was 0.47 (SD = 1.47) and for the 8 mg per kg groups was 0.34 (SD = 1.24). By the week 104, most patients in the control (placebo + MTX) group had crossed over to active treatment, and results are therefore not included for comparison. Patients in the active groups may have crossed over to the alternate active dose group, and results are reported per original randomized dose group.

In the placebo group, 66% of patients experienced no radiographic progression (Total Sharp-Genant Score change ≤ 0) at week 52 compared to 78% and 83% in the tocilizumab 4 mg per kg and 8 mg per kg, respectively. Following 104 weeks of treatment, 75% and 83% of patients initially randomized to tocilizumab 4 mg per kg and 8 mg per kg, respectively, experienced no progression of structural damage compared to 66% of placebo treated patients.

Health Related Outcomes

In Study II, physical function and disability were assessed using the Health Assessment Questionnaire Disability Index (HAQ-DI). Both dosing groups of tocilizumab demonstrated a greater improvement compared to the placebo group in the AUC of change from baseline in the HAQ-DI through week 52. The mean change from baseline to week 52 in HAQ-DI was 0.6, 0.5, and 0.4 for tocilizumab 8 mg per kg, tocilizumab 4 mg per kg, and placebo treatment groups, respectively. Sixty-three percent (63%) and sixty percent (60%) of patients in the tocilizumab 8 mg per kg and tocilizumab 4 mg per kg treatment groups, respectively, achieved a clinically relevant improvement in HAQ-DI (change from baseline of ≥ 0.3 units) at week 52 compared to 53% in the placebo treatment group.

Other Health-Related Outcomes

General health status was assessed by the Short Form Health Survey (SF-36) in Studies I – V. Patients receiving tocilizumab demonstrated greater improvement from baseline compared to placebo in the Physical Component Summary (PCS), Mental Component Summary (MCS), and in all 8 domains of the SF-36.

Cardiovascular Outcomes

Study WA25204 (NCT01331837) was a randomized, open-label (sponsor-blinded), 2-arm parallel-group, multi-center, non-inferiority, cardiovascular (CV) outcomes trial in patients with a diagnosis of moderate to severe RA. This CV safety study was designed to exclude a moderate increase in CV risk in patients treated with tocilizumab compared with a TNF inhibitor standard of care (etanercept).

The study included 3,080 seropositive RA patients with active disease and an inadequate response to non-biologic disease-modifying anti-rheumatic drugs, who were aged ≥50 years with at least one additional CV risk factor beyond RA. Patients were randomized 1:1 to IV tocilizumab 8 mg/kg Q4W or SC etanercept 50 mg QW and followed for an average of 3.2 years. The primary endpoint was the comparison of the time-to-first occurrence of any component of a composite of major adverse CV events (MACE; non-fatal myocardial infarction, non-fatal stroke, or CV death), with the final intent-to-treat analysis based on a total of 161 confirmed CV events (83/1538 [5.4%] for tocilizumab; 78/1542 [5.1%] for etanercept) reviewed by an independent and blinded adjudication committee.

Non-inferiority of tocilizumab to etanercept for cardiovascular risk was determined by excluding >80% relative increase in the risk of MACE. The estimated hazard ratio (HR) for the risk of MACE comparing tocilizumab to etanercept was 1.05; 95% CI (0.77, 1.43).

14.2 Giant Cell Arteritis - Intravenous Administration

Intravenously administered tocilizumab in patients with GCA was assessed in WP41152 (NCT03923738), an open-label PK-PD and safety study to determine the appropriate intravenous dose of tocilizumab that achieved comparable PK-PD profiles to tocilizumab by another route of administration.

At enrollment, all patients (n=24) were in remission on tocilizumab IV. In Period 1, all patients received open-label tocilizumab IV 7 mg/kg every 4 weeks for 20 weeks. Patients who completed Period 1 and remained in remission (n=22) were eligible to enter Period 2, and received open-label tocilizumab IV 6 mg/kg every 4 weeks for 20 weeks.

The efficacy of intravenous tocilizumab 6 mg/kg in adult patients with GCA is based on pharmacokinetic exposure and extrapolation to the efficacy established for tocilizumab by another route of administration in patients with GCA.

14.3 Polyarticular Juvenile Idiopathic Arthritis—Intravenous Administration

The efficacy of tocilizumab was assessed in a three-part study, WA19977 (NCT00988221), including an open-label extension in children 2 to 17 years of age with active polyarticular juvenile idiopathic arthritis (PJIA), who had an inadequate response to methotrexate or inability to tolerate methotrexate. Patients had at least 6 months of active disease (mean disease duration of 4.2 ± 3.7 years), with at least five joints with active arthritis (swollen or limitation of movement accompanied by pain and/or tenderness) and/or at least 3 active joints having limitation of motion (mean, 20 ± 14 active joints). The patients treated had subtypes of JIA that at disease onset included Rheumatoid Factor Positive or Negative Polyarticular JIA, or Extended Oligoarticular JIA. Treatment with a stable dose of methotrexate was permitted but was not required during the study. Concurrent use of disease modifying antirheumatic drugs (DMARDs), other than methotrexate, or other biologics (e.g., TNF antagonists or T cell costimulation modulator) were not permitted in the study.

Part I consisted of a 16-week active tocilizumab treatment lead-in period (n=188) followed by Part II, a 24-week randomized double-blind placebo-controlled withdrawal period, followed by Part III, a 64-week open-label period. Eligible patients weighing at or above 30 kg received tocilizumab at 8 mg/kg intravenously once every four weeks. Patients weighing less than 30 kg were randomized 1:1 to receive either tocilizumab 8 mg/kg or 10 mg/kg intravenously every four weeks. At the conclusion of the open-label Part I, 91% of patients taking background MTX in addition to tocilizumab and 83% of patients on tocilizumab monotherapy achieved an ACR 30 response at week 16 compared to baseline and entered the blinded withdrawal period (Part II) of the study. The proportions of patients with JIA ACR 50/70 responses in Part I were 84.0%, and 64%, respectively for patients taking background MTX in addition to tocilizumab and 80% and 55% respectively for patients on tocilizumab monotherapy.

In Part II, patients (ITT, n=163) were randomized to tocilizumab (same dose received in Part I) or placebo in a 1:1 ratio that was stratified by concurrent methotrexate use and concurrent corticosteroid use. Each patient continued in Part II of the study until Week 40 or until the patient satisfied JIA ACR 30 flare criteria (relative to Week 16) and qualified for escape.

The primary endpoint was the proportion of patients with a JIA ACR 30 flare at week 40 relative to week 16. JIA ACR 30 flare was defined as 3 or more of the 6 core outcome variables worsening by at least 30% with no more than 1 of the remaining variables improving by more than 30% relative to Week 16.

Tocilizumab treated patients experienced significantly fewer disease flares compared to placebo-treated patients (26% [21/82] versus 48% [39/81]; adjusted difference in proportions -21%, 95% CI: -35%, -8%).

During the withdrawal phase (Part II), more patients treated with tocilizumab showed JIA ACR 30/50/70 responses at Week 40 compared to patients withdrawn to placebo.

14.4 Systemic Juvenile Idiopathic Arthritis—Intravenous Administration

The efficacy of tocilizumab for the treatment of active SJIA was assessed in WA18221 (NCT00642460), a 12-week randomized, double blind, placebo-controlled, parallel group, 2-arm study. Patients treated with or without MTX, were randomized (tocilizumab:placebo = 2:1) to one of two treatment groups: 75 patients received tocilizumab infusions every two weeks at either 8 mg per kg for patients at or above 30 kg or 12 mg per kg for patients less than 30 kg and 37 were randomized to receive placebo infusions every two weeks. Corticosteroid tapering could occur from week six for patients who achieved a JIA ACR 70 response. After 12 weeks or at the time of escape, due to disease worsening, patients were treated with tocilizumab in the open-label extension phase at weight appropriate dosing.

The primary endpoint was the proportion of patients with at least 30% improvement in JIA ACR core set (JIA ACR 30 response) at Week 12 and absence of fever (no temperature at or above 37.5°C in the preceding 7 days). JIA ACR (American College of Rheumatology) responses are defined as the percentage improvement (e.g., 30%, 50%, 70%) in 3 of any 6 core outcome variables compared to baseline, with worsening in no more than 1 of the remaining variables by 30% or more. Core outcome variables consist of physician global assessment, parent per patient global assessment, number of joints with active arthritis, number of joints with limitation of movement, erythrocyte sedimentation rate (ESR), and functional ability (childhood health assessment questionnaire-CHAQ).

Primary endpoint result and JIA ACR response rates at Week 12 are shown in Table 8.

Table 8 Efficacy Findings at Week 12
 | Tocilizumab N=75 | Placebo N=37
Primary Endpoint: JIA ACR 30 response + absence of fever
Responders | 85% | 24%
Weighted difference (95% CI) | 62 (45, 78) | -
JIA ACR Response Rates at Week 12
JIA ACR 30
Responders | 91% | 24%
Weighted difference [The weighted difference is the difference between the tocilizumab and Placebo response rates, adjusted for the stratification factors (weight, disease duration, background oral corticosteroid dose and background methotrexate use).] (95% CI) [CI: confidence interval of the weighted difference.] | 67 (51, 83) | -
JIA ACR 50
Responders | 85% | 11%
Weighted difference (95% CI) | 74 (58, 90) | -
JIA ACR 70
Responders | 71% | 8%
Weighted difference (95% CI) | 63 (46, 80) | -

The treatment effect of tocilizumab was consistent across all components of the JIA ACR response core variables. JIA ACR scores and absence of fever responses in the open label extension were consistent with the controlled portion of the study (data available through 44 weeks).

Systemic Features

Of patients with fever or rash at baseline, those treated with tocilizumab had fewer systemic features; 35 out of 41 (85%) became fever free (no temperature recording at or above 37.5°C in the preceding 14 days) compared to 5 out of 24 (21%) of placebo-treated patients, and 14 out of 22 (64%) became free of rash compared to 2 out of 18 (11%) of placebo-treated patients. Responses were consistent in the open label extension (data available through 44 weeks).

Corticosteroid Tapering

Of the patients receiving oral corticosteroids at baseline, 8 out of 31 (26%) placebo and 48 out of 70 (69%), tocilizumab patients achieved a JIA ACR 70 response at week 6 or 8 enabling corticosteroid dose reduction. Seventeen (24%) tocilizumab patients versus 1 (3%) placebo patient were able to reduce the dose of corticosteroid by at least 20% without experiencing a subsequent JIA ACR 30 flare or occurrence of systemic symptoms to week 12. In the open label portion of the study, by week 44, there were 44 out of 103 (43%) tocilizumab patients off oral corticosteroids. Of these 44 patients 50% were off corticosteroids 18 weeks or more.

Health Related Outcomes

Physical function and disability were assessed using the Childhood Health Assessment Questionnaire Disability Index (CHAQ-DI). Seventy-seven percent (58 out of 75) of patients in the tocilizumab treatment group achieved a minimal clinically important improvement in CHAQ-DI (change from baseline of ≥ 0.13 units) at week 12 compared to 19% (7 out of 37) in the placebo treatment group.

14.5 COVID-19 - Intravenous Administration

The efficacy of tocilizumab for the treatment of COVID-19 was based on RECOVERY (NCT04381936), a randomized, controlled, open-label, platform study, and supported by the results from EMPACTA (NCT04372186), a randomized, double-blind, placebo-controlled study. Results of two other randomized, double-blind, placebo-controlled studies, COVACTA (NCT04320615) and REMDACTA (NCT04409262), which evaluated the efficacy of tocilizumab for the treatment of COVID-19 are also summarized.

RECOVERY (Randomised Evaluation of COVID-19 Therapy) Collaborative Group Study in Hospitalized Adults Diagnosed with COVID-19

RECOVERY was a randomized, controlled, open-label, multicenter platform study conducted in the United Kingdom to evaluate the efficacy and safety of potential treatments in hospitalized adult patients with severe COVID-19 pneumonia. Eligible patients for the tocilizumab portion of the study had clinically suspected or laboratory-confirmed SARS-CoV-2 infection and no medical contraindications to any of the treatments and had clinical evidence of progressive COVID-19 (defined as oxygen saturation <92% on room air or receiving oxygen therapy, and CRP ≥75 mg/L). Patients were then randomized to receive either standard of care (SoC) or intravenous tocilizumab at a weight-tiered dosing comparable to the recommended dosage [see Clinical Pharmacology (12.3)] in addition to SoC.

Efficacy analyses were performed in the intent-to-treat (ITT) population comprising 4116 adult patients who were randomized to the tocilizumab + SoC arm (n=2022) or to the SoC arm (n=2094). The mean age of participants was 64 years (range: 20 to 101), and patients were 67% male, 76% White, 11% Asian, 3% Black or African American, and 1% mixed race. At baseline, 0.2% of patients were not on supplemental oxygen, 45% of patients required low flow oxygen, 41% of patients required non-invasive ventilation or high-flow oxygen, and 14% of patients required invasive mechanical ventilation; 82% of patients were reported to be receiving systemic corticosteroids.

The primary efficacy endpoint was time to death through Day 28. The results for the overall population and the subgroups of patients who were or were not receiving systemic corticosteroids at time of randomization are summarized in Table 9.

Table 9 Mortality through Day 28 in RECOVERY
 | tocilizumab + SoC N=2022 n (%) [P-value reflects that the RECOVERY trial primary analysis results were statistically significant at the two-sided significance level of α = 0.05.] | SoC N=2094 n (%) | Hazard Ratio (95% CI) | Risk Difference (95% CI)
Mortality | 621 (30.7%) | 729 (34.9%) | 0.85 (0.76, 0.94) p= 0.0028 | -4.1% (-7.0, -1.3)
By baseline receipt of corticosteroid use
Mortality for patients receiving systemic corticosteroids at randomization [Probabilities of dying by Day 28 were estimated by the Kaplan-Meier method.] | 482/1664 (29.0%) | 600/1721 (34.9%) | 0.79 (0.70, 0.89) | -5.9% (-9.1, -2.8)
Mortality for patients not receiving systemic corticosteroids at randomization | 139/357 (39.0%) | 127/367 (34.6%) | 1.16 (0.91, 1.48) | 4.4% (-2.6, 11.5)

EMPACTA

EMPACTA was a randomized, double-blind, placebo-controlled, multicenter study to evaluate intravenous tocilizumab 8 mg/kg in combination with SoC in hospitalized, non-ventilated adult patients with COVID-19 pneumonia. Eligible patients were at least 18 years of age, had confirmed SARS-CoV-2 infection by a positive reverse-transcriptase polymerase chain reaction (RT-PCR) result, had pneumonia confirmed by radiography, and had SpO2 < 94% on ambient air.

Of the 389 patients randomized, efficacy analyses were performed in the modified intent-to-treat (mITT) population comprising 377 patients who were randomized and received study medication (249 in the tocilizumab arm; 128 in the placebo arm). The mean age of participants was 56 years (range: 20 to 95); 59% of patients were male, 56% were of Hispanic or Latino ethnicity, 53% were White, 20% were American Indian/Alaska Native, 15% were Black/African American and 2% were Asian. At baseline, 9% patients were not on supplemental oxygen, 64% patients required low flow oxygen, 27% patients required high-flow oxygen, and 73% were on corticosteroids.

The primary efficacy endpoint evaluated time to progression to mechanical ventilation or death through Day 28. The hazard ratio comparing tocilizumab to placebo was 0.56 (95% CI, 0.33 to 0.97), a statistically significant result (log-rank, p-value = 0.036). The cumulative proportion of patients who required mechanical ventilation or died by Day 28 was 12.0% (95% CI, 8.5% to 16.9%) in the tocilizumab arm and 19.3% (95% CI, 13.3% to 27.4%) in the placebo arm.

Mortality at Day 28 was 10.4% in the tocilizumab arm versus 8.6% in the placebo arm (weighted difference (tocilizumab arm - placebo arm): 2.0% [95% CI, -5.2% to 7.8%]).

COVACTA

COVACTA was a randomized, double-blind, placebo-controlled, multicenter study to evaluate intravenous tocilizumab 8 mg/kg in combination with SoC for the treatment of adult patients hospitalized with severe COVID-19 pneumonia. The study randomized 452 patients who were at least 18 years of age with confirmed SARS-CoV-2 infection by a positive RT-PCR result, had pneumonia confirmed by radiography, and had oxygen saturation of 93% or lower on ambient air or a ratio of arterial oxygen partial pressure to fractional inspired oxygen of 300 mmHg or less. At baseline, 3% of patients were not on supplemental oxygen, 28% were on low flow oxygen, 30% were on non-invasive ventilation or high flow oxygen, 38% were on invasive mechanical ventilation, and 22% were on corticosteroids. The primary efficacy endpoint was clinical status on Day 28 assessed on a 7-category ordinal scale that ranged from "discharged" to "death." There were no statistically significant differences observed in the distributions of clinical status on the 7-category ordinal scale at Day 28 when comparing the tocilizumab arm to the placebo arm.

Mortality at Day 28 was 19.7% in the tocilizumab arm versus 19.4% in the placebo arm (weighted difference (tocilizumab arm - placebo arm): 0.3% [95% CI, -7.6 to 8.2]).

REMDACTA

REMDACTA was a randomized, double-blind, placebo-controlled, multicenter study to evaluate intravenous tocilizumab 8 mg/kg in combination with intravenous remdesivir (RDV) 200 mg on Day 1 followed by 100 mg once daily for a total of 10 days in hospitalized patients with severe COVID-19 pneumonia. The study randomized 649 adult patients with SARS-CoV-2 infection confirmed by a positive polymerase chain reaction (PCR) result, pneumonia confirmed by radiography, and who required supplemental oxygen > 6 L/min to maintain SpO2 >93%. At baseline, 7% of patients were on low flow oxygen, 80% were on non-invasive ventilation or high flow oxygen, 14% were on invasive mechanical ventilation, and 84% were on corticosteroids.

The primary efficacy endpoint was time from randomization to hospital discharge or 'ready for discharge' up to Day 28. There was no statistically significant difference between the treatment arms with respect to time to hospital discharge or "ready for discharge" through Day 28.

Mortality at Day 28 was 18.1% in the tocilizumab + RDV arm versus 19.5% in the placebo +RDV arm (weighted difference (tocilizumab arm - placebo arm): -1.3% [95% CI, -7.8% to 5.2%]).

Mortality Across Studies in Patients Receiving Baseline Corticosteroids

A study-level meta-analysis was conducted on EMPACTA, COVACTA, REMDACTA and RECOVERY studies. For each of the four studies, the risk difference through Day 28 was estimated by the Kaplan-Meier method in the subgroup of patients receiving baseline corticosteroids, summarized in Figure 2. Patients from the RECOVERY trial represent 78.8% of the total sample size in this meta-analysis. The combined risk difference showed that tocilizumab treatment (n=2261) resulted in a 4.61% absolute reduction in the risk of death at Day 28 (risk difference=-4.6%; 95% CI: -7.3% to -1.9%) compared to SoC (n=2034).

Figure 2 Risk Differences Through Day 28 for Baseline Corticosteroid Use Subpopulation in RECOVERY, EMPACTA, COVACTA and REMDACTA studies

16 HOW SUPPLIED/STORAGE AND HANDLING

TOFIDENCE (tocilizumab-bavi) injection is a preservative-free, sterile, clear to opalescent, colorless to light yellow solution. TOFIDENCE is supplied as 80 mg/4 mL (NDC 64406-024-01), 200 mg/10 mL (NDC 64406-022-01), and 400 mg/20 mL (NDC 64406-023-01) individually packaged 20 mg/mL single-dose vials for further dilution prior to intravenous infusion.

Storage and Handling:Do not use beyond expiration date on the container or package. TOFIDENCE must be refrigerated at 36°F to 46°F (2°C to 8°C). Do not freeze. Protect the vials from light by storage in the original package until time of use.

17 PATIENT COUNSELING INFORMATION

Advise the patient to read the FDA-approved patient labeling (Medication Guide).

- Serious Infections

Inform patients that TOFIDENCE may lower their resistance to infections [see Warnings and Precautions (5.1)] . Instruct the patient of the importance of contacting their doctor immediately when symptoms suggesting infection appear in order to assure rapid evaluation and appropriate treatment.

- Gastrointestinal Perforation

Inform patients that some patients who have been treated with TOFIDENCE have had serious side effects in the stomach and intestines [see Warnings and Precautions (5.2)] . Instruct the patient of the importance of contacting their doctor immediately when symptoms of fever, severe, persistent abdominal pain, and change in bowel habits appear to assure rapid evaluation and appropriate treatment.

- Hypersensitivity and Serious Allergic Reactions

Inform patients that some patients who have been treated with TOFIDENCE have developed serious allergic reactions, including anaphylaxis , as well as serious skin reactions [see Warnings and Precautions (5.6)] . Advise patients to stop taking TOFIDENCE and seek immediate medical attention if they experience any symptom of serious allergic reactions (including rash, hives, and swelling of the face, lips, tongue, and throat that may cause difficulty in breathing or swallowing).

Pregnancy

Inform female patients of reproductive potential that TOFIDENCE may cause fetal harm and to inform their prescriber of a known or suspected pregnancy [see Use in Specific Populations (8.1)].

TOFIDENCE (tocilizumab-bavi)

Manufactured by:
Biogen MA Inc.
Cambridge, MA 02142
U.S. License No.: 2344

TOFIDENCE is a trademark of Biogen MA Inc.
© 2024 Biogen MA Inc. All rights reserved.

Medication Guide
TOFIDENCE™ (TOE-FIH-DENCE)
(tocilizumab-bavi) injection
for intravenous use

What is the most important information I should know about TOFIDENCE?
TOFIDENCE can cause serious side effects including:

- Serious Infections.TOFIDENCE is a medicine that affects your immune system. TOFIDENCE can lower the ability of your immune system to fight infections. Some people have serious infections while taking TOFIDENCE, including tuberculosis (TB), and infections caused by bacteria, fungi, or viruses that can spread throughout the body. Some people have died from these infections. Your healthcare provider should assess you for TB before starting TOFIDENCE (except if you have COVID-19).

If you have COVID-19, your healthcare provider should monitor you for signs and symptoms of new infections during and after treatment with TOFIDENCE.
Your healthcare provider should monitor you closely for signs and symptoms of TB during and after treatment with TOFIDENCE.

- You should not start taking TOFIDENCE if you have any kind of infection unless your healthcare provider says it is okay.

Before starting TOFIDENCE, tell your healthcare provider if you:

- think you have an infection or have symptoms of an infection, with or without a fever, such as:

- sweating or chills
- shortness of breath
- warm, red, or painful skin or sores on your body

- feel very tired
- muscle aches
- blood in phlegm
- diarrhea or stomach pain

- cough
- weight loss
- burning when you urinate or urinating more often than normal

- are being treated for an infection.
- get a lot of infections or have infections that keep coming back.
- have diabetes, HIV, or a weak immune system. People with these conditions have a higher chance for infections.
- have TB, or have been in close contact with someone with TB.
- live or have lived, or have traveled to certain parts of the country (such as the Ohio and Mississippi River valleys and the Southwest) where there is an increased chance for getting certain kinds of fungal infections (histoplasmosis, coccidiomycosis, or blastomycosis). These infections may happen or become more severe if you use TOFIDENCE. Ask your healthcare provider, if you do not know if you have lived in an area where these infections are common.
- have or have had hepatitis B.

After starting TOFIDENCE, call your healthcare provider right away if you have any symptoms of an infection. TOFIDENCE can make you more likely to get infections or make worse any infection that you have.

- Tears (perforation) of the stomach or intestines.
  - Tell your healthcare provider if you have had diverticulitis (inflammation in parts of the large intestine) or ulcers in your stomach or intestines. Some people taking TOFIDENCE get tears in their stomach or intestine. This happens most often in people who also take nonsteroidal anti-inflammatory drugs (NSAIDs), corticosteroids, or methotrexate.
  - Tell your healthcare provider right away if you have fever and new onset stomach-area pain that does not go away, and a change in your bowel habits.

- Liver problems (Hepatotoxicity):Some people have experienced serious life-threatening liver problems, which required a liver transplant or led to death. Your healthcare provider may tell you to stop taking TOFIDENCE if you develop new or worse liver problems during treatment with TOFIDENCE. Tell your healthcare provider right away if you have any of the following symptoms:

- feeling tired (fatigue)
- lack of appetite for several days or longer (anorexia)
- yellowing of your skin or the whites of your eyes (jaundice)
- abdominal swelling and pain on the right side of your stomach-area
- light colored stools

- weakness
- nausea and vomiting
- confusion
- dark "tea-colored" urine

- Changes in certain laboratory test results.Your healthcare provider should do blood tests before you start receiving TOFIDENCE. If you have rheumatoid arthritis (RA) or giant cell arteritis (GCA) your healthcare provider should do blood tests every 4 to 8 weeks after you start receiving TOFIDENCE for the first 6 months and then every 3 months after that. If you have polyarticular juvenile idiopathic arthritis (PJIA) you will have blood tests done every 4 to 8 weeks during treatment. If you have systemic juvenile idiopathic arthritis (SJIA) you will have blood tests done every 2 to 4 weeks during treatment. These blood tests are to check for the following side effects of TOFIDENCE:
  - low neutrophil count. Neutrophils are white blood cells that help the body fight off bacterial infections.
  - low platelet count. Platelets are blood cells that help with blood clotting and stop bleeding.
  - increase in certain liver function tests.
  - increase in blood cholesterol levels. You may also have changes in other laboratory tests, such as your blood cholesterol levels. Your healthcare provider should do blood tests to check your cholesterol levels 4 to 8 weeks after you start receiving TOFIDENCE.
  Your healthcare provider will determine how often you will have follow-up blood tests. Make sure you get all your follow-up blood tests done as ordered by your healthcare provider.
  You should not receive TOFIDENCE if your neutrophil or platelet counts are too low or your liver function tests are too high.
  Your healthcare provider may stop your TOFIDENCE treatment for a period of time or change your dose of medicine if needed because of changes in these blood test results.

- Cancer.TOFIDENCE may increase your risk of certain cancers by changing the way your immune system works. Tell your healthcare provider if you have ever had any type of cancer.

See " What are the possible side effects with TOFIDENCE?" for more information about side effects.

What is TOFIDENCE?
TOFIDENCE is a prescription medicine called an Interleukin-6 (IL-6) receptor antagonist. TOFIDENCE is used:

- To treat adults with moderately to severely active rheumatoid arthritis (RA), after at least one other medicine called a Disease-Modifying Anti-Rheumatic Drug (DMARD) has been used and did not work well.
- To treat adults with giant cell arteritis (GCA).
- To treat people with active PJIA ages 2 and above.
- To treat people with active SJIA ages 2 and above.
- To treat hospitalized adults with coronavirus disease 2019 (COVID-19) receiving systemic corticosteroids and requiring supplemental oxygen or mechanical ventilation.

It is not known if TOFIDENCE is safe and effective in children with PJIA or SJIA under 2 years of age or in children with conditions other than PJIA or SJIA.

Do not take TOFIDENCE:if you are allergic to tocilizumab products, or any of the ingredients in TOFIDENCE. See the end of this Medication Guide for a complete list of ingredients in TOFIDENCE.

Before you receive TOFIDENCE, tell your healthcare provider about all of your medical conditions, including if you:

- have an infection. See " What is the most important information I should know about TOFIDENCE?"
- have liver problems.
- have any stomach-area (abdominal) pain or been diagnosed with diverticulitis or ulcers in your stomach or intestines.
- have had a reaction to tocilizumab products or any of the ingredients in TOFIDENCE before.
- have or had a condition that affects your nervous system, such as multiple sclerosis.
- have recently received or are scheduled to receive a vaccine:
  - All vaccines should be brought up-to-date before starting TOFIDENCE, unless urgent treatment initiation is required.
  - People who take TOFIDENCE should not receive live vaccines.
  - People taking TOFIDENCE can receive non-live vaccines.
- plan to have surgery or a medical procedure.
- are pregnant or plan to become pregnant. TOFIDENCE may harm your unborn baby. Tell your healthcare provider if you become pregnant or think you may be pregnant during treatment with TOFIDENCE.
- are breastfeeding or plan to breastfeed. It is not known if TOFIDENCE passes into your breast milk. Talk to your healthcare provider about the best way to feed your baby if you take TOFIDENCE.

Tell your healthcare provider about all of the medicines you take,including prescription, over-the-counter medicines, vitamins and herbal supplements. TOFIDENCE and other medicines may affect each other causing side effects.
Especially tell your healthcare provider if you take:

- any other medicines to treat your RA. Taking TOFIDENCE with these medicines may increase your risk of infection.
- medicines that affect the way certain liver enzymes work. Ask your healthcare provider if you are not sure if your medicine is one of these.

Know the medicines you take. Keep a list of them to show to your healthcare provider and pharmacist when you get a new medicine.

How will I receive TOFIDENCE?
Into a vein (IV or intravenous infusion) for Rheumatoid Arthritis, Giant Cell Arteritis, PJIA, SJIA, or COVID-19:

- If your healthcare provider prescribes TOFIDENCE as an IV infusion, you will receive TOFIDENCE from a healthcare provider through a needle placed in a vein in your arm. The infusion will take about 1 hour to give you the full dose of medicine.
- For rheumatoid arthritis, giant cell arteritis or PJIA you will receive a dose of TOFIDENCE about every 4 weeks.
- For SJIA you will receive a dose of TOFIDENCE about every 2 weeks.
- For COVID-19, you will receive a single dose of TOFIDENCE, and if needed one additional dose.
- While taking TOFIDENCE, you may continue to use other medicines that help treat your rheumatoid arthritis, PJIA, SJIA, or COVID-19 such as methotrexate, non-steroidal anti-inflammatory drugs (NSAIDs) and prescription steroids, as instructed by your healthcare provider.
- Keep all of your follow-up appointments and get your blood tests as ordered by your healthcare provider.

What are the possible side effects with TOFIDENCE? TOFIDENCE can cause serious side effects, including:

- See " What is the most important information I should know about TOFIDENCE?"
- Hepatitis B infectionin people who carry the virus in their blood. If you are a carrier of the hepatitis B virus (a virus that affects the liver), the virus may become active while you use TOFIDENCE. Your healthcare provider may do blood tests before you start treatment with TOFIDENCE and while you are using TOFIDENCE. Tell your healthcare provider if you have any of the following symptoms of a possible hepatitis B infection:

- feel very tired
- vomiting
- chills
- dark urine

- skin or eyes look yellow
- clay-colored bowel movements
- stomach discomfort
- skin rash

- little or no appetite
- fevers
- muscle aches

- Serious Allergic Reactions.Serious allergic reactions, including death, can happen with TOFIDENCE. These reactions can happen with any infusion of TOFIDENCE, even if they did not occur with an earlier infusion. Stop taking TOFIDENCE, contact your healthcare provider, and get emergency help right away if you have any of the following signs of a serious allergic reaction:
  - swelling of your face, lips, mouth or tongue
  - trouble breathing
  - wheezing
  - severe itching
  - skin rash, hives, redness, or swelling outside of the injection site area
  - dizziness or fainting
  - fast heartbeat or pounding in your chest (tachycardia)
  - sweating
- Nervous system problems.While rare, Multiple Sclerosis has been diagnosed in people who take TOFIDENCE. It is not known what effect TOFIDENCE may have on some nervous system disorders.

The most common side effects of TOFIDENCE include:

- upper respiratory tract infections (common cold, sinus infections)
- headache
- increased blood pressure (hypertension)

Tell your healthcare provider about any side effect that bothers you or does not go away. These are not all the possible side effects of TOFIDENCE. For more information, ask your healthcare provider or pharmacist.
Call your doctor for medical advice about side effects. You may report side effects to FDA at 1-800-FDA-1088.
You may also report side effects to Biogen MA Inc. at 1-877-422-8360. .

General information about the safe and effective use of TOFIDENCE.
Medicines are sometimes prescribed for purposes other than those listed in a Medication Guide. Do not give TOFIDENCE to other people, even if they have the same symptoms that you have. It may harm them. You can ask your pharmacist or healthcare provider for information about TOFIDENCE that is written for health professionals.

What are the ingredients in TOFIDENCE?
Active ingredient: tocilizumab-bavi.
Inactive ingredients of Intravenous TOFIDENCE: arginine hydrochloride, histidine, L-histidine hydrochloride monohydrate,polysorbate 80, sucrose, and water for Injection.
TOFIDENCE is a trademark of Biogen MA Inc.
Manufactured by: Biogen MA Inc., Cambridge, MA 02142,U.S. License No.: 2344
© 2024 Biogen MA Inc. All rights reserved.
For more information, go to www.tofidence.com or call 1-877-422-8360 .

Medication Guide has been approved by the U.S. Food and Drug Administration

Revised: 03/2025

PRINCIPAL DISPLAY PANEL - 200 mg/10 mL Vial Carton

Rx Only
NDC 64406-022-01

Tofidence™
(tocilizumab-bavi)
Injection

200 mg/10 mL
(20 mg/mL)

For Intravenous Infusion
After Dilution.

Single-Dose Vial

Discard unused portion.

Biogen®

PRINCIPAL DISPLAY PANEL - 400 mg/20 mL Vial Carton

Rx Only
NDC 64406-023-01

Tofidence™
(tocilizumab-bavi)
Injection

400 mg/20 mL
(20 mg/mL)

For Intravenous Infusion
After Dilution.

Single-Dose Vial

Discard unused portion.

Biogen®

PRINCIPAL DISPLAY PANEL - 80 mg/4 mL Vial Carton

Rx Only
NDC 64406-024-01

Tofidence™
(tocilizumab-bavi)
Injection

80 mg/4 mL
(20 mg/mL)

For Intravenous Infusion
After Dilution.

Single-Dose Vial

Discard unused portion.

Biogen®